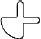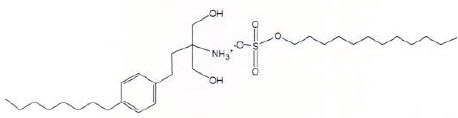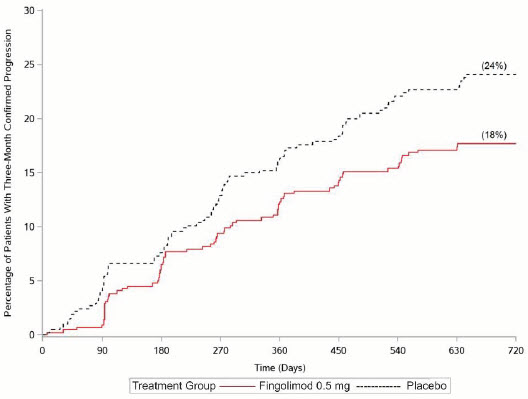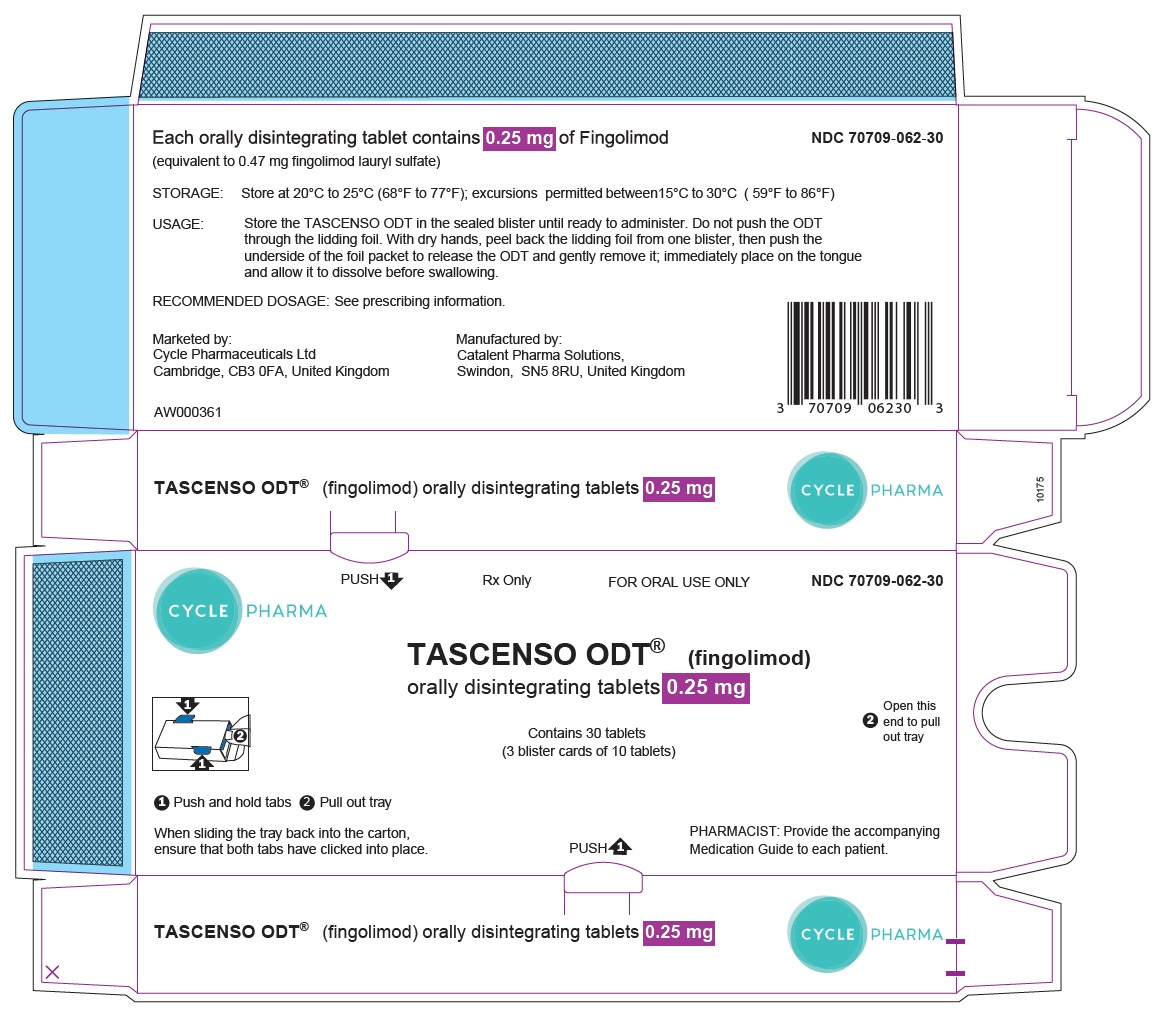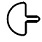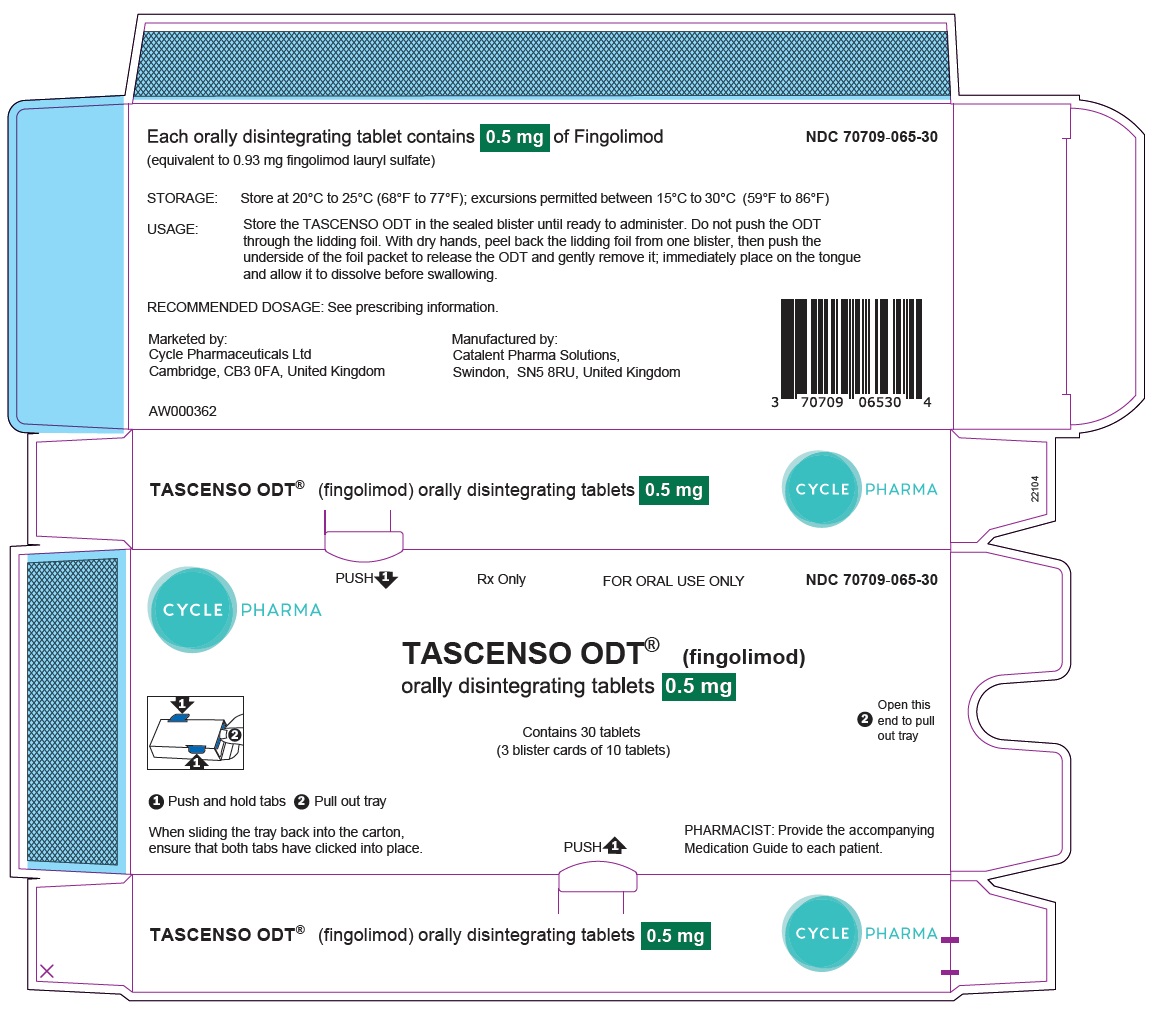 DRUG LABEL: TASCENSO ODT
NDC: 70709-062 | Form: TABLET, ORALLY DISINTEGRATING
Manufacturer: Cycle Pharmaceuticals Ltd
Category: prescription | Type: HUMAN PRESCRIPTION DRUG LABEL
Date: 20250325

ACTIVE INGREDIENTS: Fingolimod Lauryl Sulfate 0.25 mg/1 1
INACTIVE INGREDIENTS: GELATIN, UNSPECIFIED; MANNITOL; MEDIUM-CHAIN TRIGLYCERIDES; Sodium Chloride; SODIUM LAURYL SULFATE

HIGHLIGHTS OF PRESCRIBING INFORMATION

These highlights do not include all the information needed to use TASCENSO ODT® safely and effectively. See full prescribing information for TASCENSO ODT.
TASCENSO ODT (fingolimod) orally disintegrating tablets
Initial U.S. Approval: 2010

RECENT MAJOR CHANGES

Dosage and Administration (2.1) 6/2024

Dosage and Administration (2.2) 1/2025

Warnings and Precautions (5.3, 5.4, 5.12) 6/2024

1 INDICATIONS AND USAGE

TASCENSO ODT is a sphingosine 1-phosphate receptor modulator indicated for the treatment of relapsing forms of multiple sclerosis (MS), to include clinically isolated syndrome, relapsing-remitting disease, and active secondary progressive disease, in patients 10 years of age and older. (1)

2 DOSAGE AND ADMINISTRATION

- Assessments are required prior to initiating TASCENSO ODT (2.1)
- Recommended dosage for adults and pediatric patients (10 years of age and older) weighing more than 40 kg: 0.5 mg orally once daily, with or without food. (2.2, 2.3)
- Recommended dosage for pediatric patients (10 years of age and older) weighing less than or equal to 40 kg: 0.25 mg orally once daily, with or without food (2.2, 2.3).
- Administer TASCENSO ODT with or without water. Place tablet directly on the tongue and allow it to dissolve before swallowing. (2.2)
- First-Dose Monitoring (including reinitiation after discontinuation greater than 14 days and dose increases):
  - Observe all patients for bradycardia for at least 6 hours; monitor pulse and blood pressure hourly. Electrocardiograms (ECGs) prior to dosing and at end of observation period required. (2.4)
  - Monitor until resolution if heart rate < 45 beats per minute (bpm) in adults, < 55 bpm in patients aged 12 years and above, or < 60 bpm in pediatric patients aged 10 to below 12 years, atrioventricular (AV) block, or if lowest postdose heart rate is at the end of the observation period. (2.4)
  - Monitor symptomatic bradycardia with ECG until resolved. Continue overnight if intervention is required; repeat first-dose monitoring for second dose. (2.4)
  - Observe patients overnight if at higher risk of symptomatic bradycardia, heart block, prolonged QTc interval, or if taking drugs with known risk of torsades de pointes. (2.4, 7.1)

3 DOSAGE FORMS AND STRENGTHS

Orally disintegrating tablets: 0.25 mg and 0.5 mg (3)

4 CONTRAINDICATIONS

- Recent myocardial infarction, unstable angina, stroke, transient ischemic attack, decompensated heart failure with hospitalization, or Class III/IV heart failure. (4)
- History of Mobitz Type II 2nd degree or 3rd degree AV block or sick sinus syndrome, unless patient has a pacemaker. (4)
- Baseline QTc interval ≥ 500 msec. (4)
- Cardiac arrhythmias requiring anti-arrhythmic treatment with Class Ia or Class III anti-arrhythmic drugs. (4)
- Hypersensitivity to fingolimod or its excipients. (4)
- Concomitant use with other products containing fingolimod. (4)

5 WARNINGS AND PRECAUTIONS

- Bradyarrhythmia and Atrioventricular Blocks: Because of a risk for bradyarrhythmia and AV blocks, monitor during initiation of treatment (2.4, 5.1)
- Infections: TASCENSO ODT may increase the risk. Obtain a complete blood count (CBC) before initiating TASCENSO ODT (i.e., within 6 months). Monitor for infection during treatment and for 2 months after discontinuation. Do not start in patients with active infections. (5.2)
- Progressive Multifocal Leukoencephalopathy (PML): Withhold TASCENSO ODT at the first sign or symptom suggestive of PML. (5.3)
- Macular Edema: Increases the risk of macular edema. Obtain a baseline evaluation of the fundus, including the macula, near the start of treatment with TASCENSO ODT. Conduct an evaluation of the fundus, including the macula, 3 to 4 months after treatment start, periodically while on therapy, and any time there is a change in vision. Consider discontinuing TASCENSO ODT if macular edema develops. Diabetes mellitus and uveitis increase the risk. (5.4)
- Liver Injury: Obtain liver enzyme results before initiation and periodically during treatment. Closely monitor patients with severe hepatic impairment. Discontinue if there is evidence of liver injury without other cause. (5.5, 8.6, 12.3)
- Posterior Reversible Encephalopathy Syndrome (PRES): If suspected, discontinue TASCENSO ODT. (5.6)
- Respiratory Effects: Evaluate when clinically indicated. (5.7)
- Fetal Risk: May cause fetal harm. Advise females of reproductive potential of the potential risk to a fetus and to use an effective method of contraception during treatment and for 2 months after stopping TASCENSO ODT. (5.8, 8.1, 8.3)
- Severe Increase in Disability After Stopping TASCENSO ODT: Monitor for development of severe increase in disability following discontinuation and begin appropriate treatment as needed. (5.9)
- Tumefactive MS: Consider when severe MS relapse occurs during treatment or after discontinuation. Obtain imaging and begin treatment as needed. (5.10)
- Increased Blood Pressure (BP): Monitor BP during treatment. (5.11)
- Malignancies: Skin examination prior to or shortly after the start of treatment and periodically thereafter is recommended. Suspicious skin lesions should be evaluated. (5.12)

6 ADVERSE REACTIONS

Most common adverse reactions (incidence ≥ 10% and greater than placebo): Headache, liver transaminase elevation, diarrhea, cough, influenza, sinusitis, back pain, abdominal pain, and pain in extremity. (6.1)

To report SUSPECTED ADVERSE REACTIONS, contact Cycle Pharmaceuticals Ltd at 1-888-533-1625 or FDA at 1-800-FDA-1088 or www.fda.gov/medwatch.

7 DRUG INTERACTIONS

- Systemic Ketoconazole: Monitor during concomitant use. (7.2, 12.3)
- Vaccines: Avoid live attenuated vaccines during, and for 2 months after stopping TASCENSO ODT treatment. (5.3, 7.3)

FULL PRESCRIBING INFORMATION

1 INDICATIONS AND USAGE

TASCENSO ODT is indicated for the treatment of relapsing forms of multiple sclerosis (MS), to include clinically isolated syndrome, relapsing-remitting disease, and active secondary progressive disease, in patients 10 years of age and older.

2 DOSAGE AND ADMINISTRATION

2.1 Assessment Prior to Initiating TASCENSO ODT

Cardiac Evaluation

Obtain a cardiac evaluation in patients with certain preexisting conditions [see Dosage and Administration (2.4) and Warnings and Precautions (5.1)].

Prior to starting treatment, determine whether patients are taking drugs that could slow heart rate or atrioventricular (AV) conduction [see Dosage and Administration (2.4), Drug Interactions (7.5)].

Complete Blood Count (CBC)

Review results of a recent CBC [see Warnings and Precautions (5.2), Drug Interactions (7.6)].

Serum Transaminases (ALT and AST) and Total Bilirubin Levels

Prior to starting treatment with TASCENSO ODT (i.e., within 6 months), review serum transaminases [alanine transaminase (ALT) and aspartate transferase (AST)] and total bilirubin levels [see Warnings and Precautions (5.5)].

Ophthalmic Assessment

Obtain a baseline evaluation of the fundus, including the macula, near the start of treatment with TASCENSO ODT [see Warnings and Precautions (5.4)].

Skin Examination

Obtain a baseline skin examination prior to or shortly after initiation of TASCENSO ODT. If a suspicious skin lesion is observed, it should be promptly evaluated [see Warnings and Precautions (5.12)].

Prior Medications

If patients are taking antineoplastic, immunosuppressive, or immune-modulating therapies, or if there is a history of prior use of these drugs, consider possible unintended additive immunosuppressive effects prior to initiating treatment with TASCENSO ODT [see Warnings and Precautions (5.2), Drug Interactions (7.4)].

Vaccinations

Prior to initiating TASCENSO ODT, test patients for antibodies to varicella zoster virus (VZV). VZV vaccination of antibody- negative patients is recommended prior to commencing treatment with TASCENSO ODT [see Warnings and Precautions (5.2)]. It is recommended that pediatric patients if possible, complete all other immunizations in accordance with current immunization guidelines prior to initiating TASCENSO ODT.

2.2 Important Administration Instructions

Patients who initiate TASCENSO ODT, and those who reinitiate treatment after discontinuation for longer than 14 days, require first- dose monitoring. This monitoring is also recommended when the dose is increased in pediatric patients. Patients who are currently treated with another fingolimod product and underwent first-dose monitoring at initiation may be switched to TASCENSO ODT at the same daily dose without a need to repeat first-dose monitoring (unless the previous treatment was discontinued more than 14 days prior) [see Dosage and Administration (2.4, 2.5)].

TASCENSO ODT can be taken with or without food.

Inform the patient about the following administration instructions for TASCENSO ODT:

- Store the orally disintegrating tablet (ODT) in the sealed blister until ready to administer.
- Do not push the ODT through the lidding foil.
- Use dry hands when opening the blister pack.
- Peel back the lidding foil from one blister, then push the underside of the foil packet to release the ODT and gently remove the ODT.
- Take the ODT immediately after opening the blister pack.
- Place the ODT on the tongue and allow it to dissolve before swallowing.
- The ODT may be taken with or without water.

2.3 Recommended Dosage

In adults and pediatric patients 10 years of age and older weighing more than 40 kg, the recommended dosage of TASCENSO ODT is 0.5 mg orally once-daily.

In pediatric patients 10 years of age and older weighing less than or equal to 40 kg, the recommended dosage of TASCENSO ODT is 0.25 mg orally once daily.

Fingolimod doses higher than 0.5 mg are associated with a greater incidence of adverse reactions without additional benefit.

2.4 First-Dose Monitoring

Initiation of TASCENSO ODT treatment results in a decrease in heart rate, for which monitoring is recommended [see Warnings and Precautions (5.1), Clinical Pharmacology (12.2)]. Prior to dosing and at the end of the observation period, obtain an electrocardiogram (ECG) in all patients.

First 6-Hour Monitoring

Administer the first dose of TASCENSO ODT in a setting in which resources to appropriately manage symptomatic bradycardia are available. Monitor all patients for 6 hours after the first dose for signs and symptoms of bradycardia with hourly pulse and blood pressure measurement.

Additional Monitoring after 6-Hour Monitoring

Continue monitoring until the abnormality resolves if any of the following is present (even in the absence of symptoms) after 6 hours:

- The heart rate 6 hours postdose is less than 45 bpm in adults, less than 55 bpm in pediatric patients 12 years of age and older, or less than 60 bpm in pediatric patients 10 or 11 years of age
- The heart rate 6 hours postdose is at the lowest value postdose suggesting that the maximum pharmacodynamic effect on the heart may not have occurred
- The ECG 6 hours postdose shows new onset second degree or higher AV block.

If postdose symptomatic bradycardia occurs, initiate appropriate management, begin continuous ECG monitoring, and continue monitoring until the symptoms have resolved if no pharmacological treatment is required. If pharmacological treatment is required, continue monitoring overnight and repeat 6-hour monitoring after the second dose.

Overnight Monitoring

Continuous overnight ECG monitoring in a medical facility should be instituted:

- in patients that require pharmacologic intervention for symptomatic bradycardia. In these patients, the first-dose monitoring strategy should be repeated after the second dose of TASCENSO ODT
- in patients with some preexisting heart and cerebrovascular conditions [see Warnings and Precautions (5.1)]
- in patients with a prolonged QTc interval before dosing or during 6-hour observation, or at additional risk for QT prolongation, or on concurrent therapy with QT prolonging drugs with a known risk of torsades de pointes [see Warnings and Precautions (5.1), Drug Interactions (7.1)]
- in patients receiving concurrent therapy with drugs that slow heart rate or AV conduction [see Drug Interactions (7.5)].

2.5 Monitoring After Reinitiation of Therapy Following Discontinuation

When restarting TASCENSO ODT treatment after discontinuation for more than 14 days after the first month of treatment, perform first-dose monitoring, because effects on heart rate and AV conduction may recur on reintroduction of TASCENSO ODT treatment [see Dosage and Administration (2.4)]. The same precautions (first-dose monitoring) as for initial dosing are applicable. Within the first 2 weeks of treatment, first-dose procedures are recommended after interruption of 1 day or more; during Weeks 3 and 4 of treatment, first-dose procedures are recommended after treatment interruption of more than 7 days.

3 DOSAGE FORMS AND STRENGTHS

TASCENSO ODT is available as:

- 0.25 mg orally disintegrating tablets are white to off white, round tablets debossed with .
- 0.5 mg orally disintegrating tablets are white to off white, round tablets debossed with .

4 CONTRAINDICATIONS

TASCENSO ODT is contraindicated in patients who have:

- in the last 6 months experienced myocardial infarction, unstable angina, stroke, TIA, decompensated heart failure requiring hospitalization or Class III/IV heart failure
- a history or presence of Mobitz Type II second-degree or third-degree AV block or sick sinus syndrome, unless patient has a functioning pacemaker [see Warnings and Precautions (5.1)]
- a baseline QTc interval ≥ 500 msec
- cardiac arrhythmias requiring anti-arrhythmic treatment with Class Ia or Class III anti-arrhythmic drugs
- had a hypersensitivity reaction to fingolimod or any of the excipients in TASCENSO ODT. Observed reactions include rash, urticaria, and angioedema [see Warnings and Precautions (5.14)].
- Concomitant use with other products containing fingolimod

5 WARNINGS AND PRECAUTIONS

5.1 Bradyarrhythmia and Atrioventricular Blocks

Because of a risk for bradyarrhythmia and AV blocks, patients should be monitored during TASCENSO ODT treatment initiation [see Dosage and Administration (2.4)].

Reduction in Heart Rate

After the first dose of TASCENSO ODT, the heart rate decrease starts within an hour. On Day 1, the maximum decline in heart rate generally occurs within 6 hours and recovers, although not to baseline levels, by 8 to 10 hours postdose. Because of physiological diurnal variation, there is a second period of heart rate decrease within 24 hours after the first dose. In some patients, heart rate decrease during the second period is more pronounced than the decrease observed in the first 6 hours. Heart rates below 40 beats per minute (bpm) in adults, and below 50 bpm in pediatric patients occurred rarely. In controlled clinical trials in adult patients, adverse reactions of symptomatic bradycardia following the first dose were reported in 0.6% of patients receiving fingolimod 0.5 mg and in 0.1% of patients on placebo. Patients who experienced bradycardia were generally asymptomatic, but some patients experienced hypotension, dizziness, fatigue, palpitations, and/or chest pain that usually resolved within the first 24 hours on treatment.

Patients with some preexisting conditions (e.g., ischemic heart disease, history of myocardial infarction, congestive heart failure, history of cardiac arrest, cerebrovascular disease, uncontrolled hypertension, history of symptomatic bradycardia, history of recurrent syncope, severe untreated sleep apnea, AV block, sinoatrial heart block) may poorly tolerate the TASCENSO ODT-induced bradycardia, or experience serious rhythm disturbances after the first dose of TASCENSO ODT. Prior to treatment with TASCENSO ODT, these patients should have a cardiac evaluation by a physician appropriately trained to conduct such evaluation, and if treated with TASCENSO ODT, should be monitored overnight with continuous ECG in a medical facility after the first dose.

Since initiation of TASCENSO ODT treatment results in decreased heart rate and may prolong the QT interval, patients with a prolonged QTc interval (> 450 msec adult and pediatric males, > 470 msec adult females, or > 460 msec pediatric females) before dosing or during 6-hour observation, or at additional risk for QT prolongation (e.g., hypokalemia, hypomagnesemia, congenital long- QT syndrome), or on concurrent therapy with QT prolonging drugs with a known risk of torsades de pointes (e.g., citalopram, chlorpromazine, haloperidol, methadone, erythromycin) should be monitored overnight with continuous ECG in a medical facility.

Following the second fingolimod dose, a further decrease in heart rate may occur when compared to the heart rate prior to the second dose, but this change is of a smaller magnitude than that observed following the first dose. With continued fingolimod dosing, the heart rate returns to baseline within 1 month of chronic treatment. Clinical data indicate effects of TASCENSO ODT on heart rate are maximal after the first dose although milder effects on heart rate may persist for, on average, 2 to 4 weeks after initiation of therapy at which time heart rate generally returns to baseline. Physicians should continue to be alert to patient reports of cardiac symptoms.

Atrioventricular Blocks

Initiation of TASCENSO ODT treatment has resulted in transient AV conduction delays. In controlled clinical trials in adult patients, first-degree AV block after the first dose occurred in 4.7% of patients receiving fingolimod capsules and 1.6% of patients on placebo. In a study of 697 patients with available 24-hour Holter monitoring data after their first dose (N = 351 receiving fingolimod capsules and N = 346 on placebo), second-degree AV blocks (Mobitz Types I [Wenckebach] or 2:1 AV blocks) occurred in 4% (N = 14) of patients receiving fingolimod capsules and 2% (N = 7) of patients on placebo. Of the 14 patients receiving fingolimod capsules, 7 patients had 2:1 AV block (5 patients within the first 6 hours postdose and 2 patients after 6 hours postdose). All second-degree AV blocks on placebo were Mobitz Type I and occurred after the first 12 hours postdose. The conduction abnormalities were usually transient and asymptomatic, and resolved within the first 24 hours on treatment, but they occasionally required treatment with atropine or isoproterenol.

Postmarketing Experience

In the postmarketing setting, third-degree AV block and AV block with junctional escape have been observed during the first-dose 6-hour observation period with fingolimod. Isolated delayed onset events, including transient asystole and unexplained death, have occurred within 24 hours of the first dose. These events were confounded by concomitant medications and/or preexisting disease, and the relationship to fingolimod is uncertain. Cases of syncope were also reported after the first dose of fingolimod.

5.2 Infections

Risk of Infections

TASCENSO ODT causes a dose-dependent reduction in peripheral lymphocyte count to 20%-30% of baseline values because of reversible sequestration of lymphocytes in lymphoid tissues. TASCENSO ODT may therefore increase the risk of infections, some serious in nature [see Clinical Pharmacology (12.2)]. Life-threatening and fatal infections have occurred in association with fingolimod, the active moiety in TASCENSO ODT.

Before initiating treatment with TASCENSO ODT, results from a recent CBC (i.e., within 6 months or after discontinuation of prior therapy) should be reviewed. Initiation of treatment with TASCENSO ODT should be delayed in patients with severe active infection until resolution. Because residual pharmacodynamic effects, such as lowering effects on peripheral lymphocyte count, may persist for up to 2 months after discontinuation of TASCENSO ODT, vigilance for infection should be continued throughout this period [see Warnings and Precautions (5.13)].

In MS placebo-controlled trials in adult patients treated with fingolimod capsules, the overall rate of infections (72%) with fingolimod capsules was similar to placebo. However, bronchitis, herpes zoster, influenza, sinusitis, and pneumonia were more common in fingolimod-treated patients. Serious infections occurred at a rate of 2.3% in the fingolimod group versus 1.6% in the placebo group.

In the postmarketing setting, serious infections with opportunistic pathogens including viruses (e.g., John Cunningham virus (JCV), herpes simplex viruses 1 and 2, varicella zoster virus), fungi (e.g., cryptococci), and bacteria (e.g., atypical mycobacteria) have been reported with fingolimod. Patients with symptoms and signs consistent with any of these infections should undergo prompt diagnostic evaluation and appropriate treatment.

Herpes Viral Infections

In placebo-controlled trials in adult patients treated with fingolimod capsules, the rate of herpetic infections was 9% in patients receiving fingolimod 0.5 mg and 7% on placebo.

Two patients died of herpetic infections during controlled trials. One death was due to disseminated primary herpes zoster and the other was to herpes simplex encephalitis. In both cases, the patients were taking a 1.25 mg dose of fingolimod (higher than the recommended 0.5 mg dose) and had received high-dose corticosteroid therapy to treat suspected MS relapses.

Serious, life-threatening events of disseminated varicella zoster and herpes simplex infections, including cases of encephalitis and multiorgan failure, have occurred with fingolimod in the postmarketing setting. Include disseminated herpetic infections in the differential diagnosis of patients who are receiving TASCENSO ODT and present with an atypical MS relapse or multiorgan failure.

Cases of Kaposi's sarcoma have been reported in patients treated with fingolimod in the postmarketing setting. Kaposi's sarcoma is an angioproliferative disorder that is associated with infection with human herpes virus 8 (HHV-8). Patients with symptoms or signs consistent with Kaposi's sarcoma should be referred for prompt diagnostic evaluation and management.

Cryptococcal Infections

Cryptococcal infections, including cases of fatal cryptococcal meningitis and disseminated cryptococcal infections, have been reported with fingolimod in the postmarketing setting. Cryptococcal infections have generally occurred after approximately 2 years of fingolimod treatment but may occur earlier. The relationship between the risk of cryptococcal infection and the duration of treatment is unknown. Patients with symptoms and signs consistent with a cryptococcal infection should undergo prompt diagnostic evaluation and treatment.

Prior and Concomitant Treatment with Antineoplastic, Immunosuppressive, or Immune-Modulating Therapies

In clinical studies, patients who received fingolimod capsules did not receive concomitant treatment with antineoplastic, non- corticosteroid immunosuppressive, or immune-modulating therapies used for treatment of MS. Concomitant use of TASCENSO ODT with any of these therapies, and also with corticosteroids, would be expected to increase the risk of immunosuppression [see Drug Interactions (7.4)].

When switching to fingolimod from immune-modulating or immunosuppressive medications, consider the duration of their effects and their mode of action to avoid unintended additive immunosuppressive effects.

Varicella Zoster Virus Antibody Testing/Vaccination

Patients without a healthcare professional confirmed history of chickenpox or without documentation of a full course of vaccination against VZV should be tested for antibodies to VZV before initiating TASCENSO ODT. VZV vaccination of antibody-negative patients is recommended prior to commencing treatment with TASCENSO ODT, following which initiation of treatment with TASCENSO ODT should be postponed for 1 month to allow the full effect of vaccination to occur [see Drug Interactions (7.3), Use in Specific Populations (8.4)].

Human Papilloma Virus Infection

Human papilloma virus (HPV) infections, including papilloma, dysplasia, warts, and HPV-related cancer, have been reported in patients treated with fingolimod in the postmarketing setting. Vaccination against HPV should be considered prior to treatment initiation with TASCENSO ODT, taking into account vaccination recommendations. Cancer screening, including Papanicolaou (Pap) test, is recommended as per standard of care for patients using an immunosuppressive therapy.

5.3 Progressive Multifocal Leukoencephalopathy

Cases of progressive multifocal leukoencephalopathy (PML) have occurred in patients with MS who received fingolimod, the active moiety in TASCENSO ODT, in the postmarketing setting. PML is an opportunistic viral infection of the brain caused by the JC virus (JCV) that typically only occurs in patients who are immunocompromised, and that usually leads to death or severe disability. PML has occurred in patients who had not been treated previously with natalizumab, which has a known association with PML, were not taking any other immunosuppressive or immunomodulatory medications concomitantly and did not have any ongoing systemic medical conditions resulting in compromised immune system function. Longer treatment duration increases the risk of PML in fingolimod-treated patients; the majority of cases have occurred in patients treated with fingolimod for at least 18 months.

At the first sign or symptom suggestive of PML, withhold TASCENSO ODT and perform an appropriate diagnostic evaluation. Typical symptoms associated with PML are diverse, progress over days to weeks, and include progressive weakness on one side of the body or clumsiness of limbs, disturbance of vision, and changes in thinking, memory, and orientation leading to confusion and personality changes.

Magnetic resonance imaging (MRI) findings may be apparent before clinical signs or symptoms. Cases of PML, diagnosed based on MRI findings and the detection of JCV DNA in the cerebrospinal fluid in the absence of clinical signs or symptoms specific to PML, have been reported in patients treated with MS medications associated with PML, including fingolimod. Many of these patients subsequently became symptomatic with PML. Therefore, monitoring with MRI for signs that may be consistent with PML may be useful, and any suspicious findings should lead to further investigation to allow for an early diagnosis of PML, if present. Lower PML-related mortality and morbidity have been reported following discontinuation of another MS medication associated with PML in patients with PML who were initially asymptomatic compared to patients with PML who had characteristic clinical signs and symptoms at diagnosis. It is not known whether these differences are due to early detection and discontinuation of MS treatment or due to differences in disease in these patients.

If PML is confirmed, treatment with TASCENSO ODT should be discontinued.

Immune reconstitution inflammatory syndrome (IRIS) has been reported in patients treated with S1P receptor modulators, including fingolimod, who developed PML and subsequently discontinued treatment. IRIS presents as a clinical decline in the patient’s condition that may be rapid, can lead to serious neurological complications or death, and is often associated with characteristic changes on MRI. The time to onset of IRIS in patients with PML was generally within a few months after S1P receptor modulator discontinuation. Monitoring for development of IRIS and appropriate treatment of the associated inflammation should be undertaken.

5.4 Macular Edema

S1P receptor modulators, including TASCENSO ODT, have been associated with an increased risk of macular edema. Obtain a baseline evaluation of the fundus, including the macula, near the start of treatment with TASCENSO ODT. Perform an examination of the fundus, including the macula, 3 to 4 months after starting treatment, periodically while on therapy, and any time there is a change in vision.

A dose-dependent increase in the risk of macular edema occurred in the fingolimod capsules clinical development program.

In 2-year double-blind, placebo-controlled studies in adult patients with multiple sclerosis, macular edema with or without visual symptoms occurred in 1.5% of patients (11/799) treated with fingolimod 1.25 mg capsules, 0.5% of patients (4/783) treated with fingolimod 0.5 mg capsules, and 0.4% of patients (3/773) treated with placebo. Macular edema occurred predominantly during the first 3 to 4 months of therapy. These clinical trials excluded patients with diabetes mellitus, a known risk factor for macular edema (see below Macular Edema in Patients with History of Uveitis or Diabetes Mellitus). Symptoms of macular edema included blurred vision and decreased visual acuity. Routine ophthalmological examination detected macular edema in some patients with no visual symptoms. Macular edema generally partially or completely resolved with or without treatment after drug discontinuation. Some patients had residual visual acuity loss even after resolution of macular edema. Macular edema has also been reported in patients taking fingolimod in the postmarketing setting, usually within the first 6 months of treatment.

Continuation of TASCENSO ODT in patients who develop macular edema has not been evaluated. Macular edema over an extended period of time (i.e., 6 months) can lead to permanent visual loss. Consider discontinuing TASCENSO ODT if macular edema develops; this decision should include an assessment of the potential benefits and risks for the individual patient. The risk of recurrence after rechallenge has not been evaluated.

Macular Edema in Patients with History of Uveitis or Diabetes Mellitus

Patients with a history of uveitis and patients with diabetes mellitus are at increased risk of macular edema during TASCENSO ODT therapy. In the combined clinical trial experience in adult patients with all doses of fingolimod capsules, the rate of macular edema was higher in MS patients with a history of uveitis compared to those without a history of uveitis (approximately 20% versus 0.6%, respectively). Fingolimod, the active moiety in TASCENSO ODT, has not been tested in MS patients with diabetes mellitus.

5.5 Liver Injury

Clinically significant liver injury has occurred in patients treated with fingolimod in the postmarketing setting. Signs of liver injury, including markedly elevated serum hepatic enzymes and elevated total bilirubin, have occurred as early as ten days after the first dose and have also been reported after prolonged use. Cases of acute liver failure requiring liver transplant have been reported.

In 2-year placebo-controlled clinical trials in adult patients, elevation of liver enzymes (ALT, AST and GGT) to 3-fold the upper limit of normal (ULN) or greater occurred in 14% of patients treated with fingolimod 0.5 mg capsules and 3% of patients on placebo. Elevations 5-fold the ULN or greater occurred in 4.5% of patients on fingolimod capsules and 1% of patients on placebo. The majority of elevations occurred within 6 to 9 months. In clinical trials, fingolimod capsules were discontinued if the elevation exceeded 5 times the ULN. Serum transaminase levels returned to normal within approximately 2 months after discontinuation of fingolimod capsules. Recurrence of liver transaminase elevations occurred with rechallenge in some patients.

Prior to starting treatment with TASCENSO ODT (within 6 months), obtain serum transaminases (ALT and AST) and total bilirubin levels. Obtain transaminase levels and total bilirubin levels periodically until two months after TASCENSO ODT discontinuation.

Patients should be monitored for signs and symptoms of any hepatic injury. Measure liver transaminase and bilirubin levels promptly in patients who report symptoms that may indicate liver injury, including new or worsening fatigue, anorexia, right upper abdominal discomfort, dark urine, or jaundice. In this clinical context, if the patient is found to have an alanine aminotransferase (ALT) greater than three times the reference range with serum total bilirubin greater than two times the reference range, treatment with TASCENSO ODT treatment should be interrupted. Treatment should not be resumed if a plausible alternative etiology for the signs and symptoms cannot be established, because these patients are at risk for severe drug-induced liver injury.

Because fingolimod exposure is doubled in patients with severe hepatic impairment, these patients should be closely monitored during treatment with TASCENSO ODT, as the risk of adverse reactions is greater [see Use in Specific Populations (8.6), Clinical Pharmacology (12.3)].

5.6 Posterior Reversible Encephalopathy Syndrome

There have been rare cases of posterior reversible encephalopathy syndrome (PRES) reported in adult patients receiving fingolimod. Symptoms reported included sudden onset of severe headache, altered mental status, visual disturbances, and seizure. Symptoms of PRES are usually reversible but may evolve into ischemic stroke or cerebral hemorrhage. Delay in diagnosis and treatment may lead to permanent neurological sequelae. If PRES is suspected, TASCENSO ODT should be discontinued.

5.7 Respiratory Effects

Dose-dependent reductions in forced expiratory volume over 1 second (FEV1) and diffusion lung capacity for carbon monoxide (DLCO) were observed in patients treated with fingolimod, the active moiety in TASCENSO ODT, as early as 1 month after treatment initiation. In 2-year placebo-controlled trials in adult patients, the reduction from baseline in the percent of predicted values for FEV1 at the time of last assessment on drug was 2.8% for fingolimod 0.5 mg capsules and 1.0% for placebo. For DLCO, the reduction from baseline in percent of predicted values at the time of last assessment on drug was 3.3% for fingolimod 0.5 mg capsules and 0.5% for placebo. The changes in FEV1 appear to be reversible after treatment discontinuation. There is insufficient information to determine the reversibility of the decrease of DLCO after drug discontinuation. In MS placebo-controlled trials in adult patients, dyspnea was reported in 9% of patients receiving fingolimod 0.5 mg capsules and 7% of patients receiving placebo. Several patients discontinued fingolimod capsules because of unexplained dyspnea during the extension (uncontrolled) studies. Fingolimod, the active moiety in TASCENSO ODT, has not been tested in MS patients with compromised respiratory function.

Spirometric evaluation of respiratory function and evaluation of DLCO should be performed during therapy with TASCENSO ODT if clinically indicated.

5.8 Fetal Risk

Based on findings from animal studies, TASCENSO ODT may cause fetal harm when administered to a pregnant woman. In animal reproduction studies conducted in rats and rabbits, developmental toxicity was observed with administration of fingolimod at doses less than the recommended human dose. Advise pregnant women and females of reproductive potential of the potential risk to a fetus. Because it takes approximately 2 months to eliminate fingolimod from the body, advise females of reproductive potential to use effective contraception to avoid pregnancy during and for 2 months after stopping TASCENSO ODT treatment [see Use in Specific Populations (8.1, 8.3)].

5.9 Severe Increase in Disability After Stopping TASCENSO ODT

Severe increase in disability accompanied by multiple new lesions on MRI has been reported after discontinuation of fingolimod in the postmarketing setting. Patients in most of these reported cases did not return to the functional status they had before stopping fingolimod. The increase in disability generally occurred within 12 weeks after stopping fingolimod but was reported up to 24 weeks after fingolimod discontinuation.

Monitor patients for development of severe increase in disability following discontinuation of TASCENSO ODT and begin appropriate treatment as needed.

After stopping TASCENSO ODT in the setting of PML, monitor for development of immune reconstitution inflammatory syndrome (PML-IRIS) [see Warnings and Precautions (5.3)].

5.10 Tumefactive Multiple Sclerosis

MS relapses with tumefactive demyelinating lesions on imaging have been observed during fingolimod therapy and after fingolimod discontinuation in the postmarketing setting. Most reported cases of tumefactive MS in patients receiving fingolimod have occurred within the first 9 months after fingolimod initiation, but tumefactive MS may occur at any point during treatment. Cases of tumefactive MS have also been reported within the first 4 months after fingolimod discontinuation.

Tumefactive MS should be considered when a severe MS relapse occurs during TASCENSO ODT treatment, especially during initiation, or after discontinuation of TASCENSO ODT, prompting imaging evaluation and initiation of appropriate treatment.

5.11 Increased Blood Pressure

In adult MS controlled clinical trials, patients treated with fingolimod 0.5 mg capsules had an average increase over placebo of approximately 3 mmHg in systolic pressure, and approximately 2 mmHg in diastolic pressure, first detected after approximately 1 month of fingolimod treatment initiation and persisting with continued treatment. Hypertension was reported as an adverse reaction in 8% of patients on fingolimod 0.5 mg capsules and in 4% of patients on placebo. Blood pressure should be monitored during treatment with TASCENSO ODT.

5.12 Malignancies

Cutaneous Malignancies

The risk of cutaneous malignancies (including basal cell carcinoma (BCC), squamous cell carcinoma (SCC), and melanoma) is increased in patients treated with S1P receptor modulators. Use of fingolimod, the active moiety in TASCENSO ODT, has been associated with an increased risk of BCC and melanoma.

In two-year placebo-controlled trials in adult patients, the incidence of BCC was 2% in patients on fingolimod 0.5 mg capsules and 1% in patients on placebo [see Adverse Reactions (6.1)]. Melanoma, basal cell carcinoma, squamous cell carcinoma, Kaposi’s sarcoma [see Warnings and Precautions (5.2)], and Merkel cell carcinoma have been reported with fingolimod in the postmarketing setting.

Skin examinations are recommended prior to or shortly after the start of treatment and periodically thereafter for all patients, particularly those with risk factors for skin cancer. Providers and patients are advised to monitor for suspicious skin lesions. If a suspicious skin lesion is observed, it should be promptly evaluated. As usual for patients with increased risk for skin cancer, exposure to sunlight and ultraviolet light should be limited by wearing protective clothing and using a sunscreen with a high protection factor. Concomitant phototherapy with UV-B radiation or PUVA photochemotherapy is not recommended in patients taking TASCENSO ODT.

Lymphoma

Cases of lymphoma, including both T-cell and B-cell types and CNS lymphoma, have occurred in patients receiving fingolimod, the active moiety in TASCENSO ODT. The reporting rate of non-Hodgkin lymphoma with fingolimod is greater than that expected in the general population adjusted by age, gender, and region. Cutaneous T-cell lymphoma (including mycosis fungoides) has also been reported with fingolimod in the postmarketing setting.

5.13 Immune System Effects Following TASCENSO ODT Discontinuation

Fingolimod remains in the blood and has pharmacodynamic effects, including decreased lymphocyte counts, for up to 2 months following the last dose of TASCENSO ODT. Lymphocyte counts generally return to the normal range within 1 to 2 months of stopping therapy [see Clinical Pharmacology (12.2)]. Because of the continuing pharmacodynamic effects of fingolimod, initiating other drugs during this period warrants the same considerations needed for concomitant administration (e.g., risk of additive immunosuppressant effects) [see Drug Interactions (7.4)].

5.14 Hypersensitivity Reactions

Hypersensitivity reactions, including rash, urticaria, and angioedema have been reported with fingolimod in the postmarketing setting. TASCENSO ODT is contraindicated in patients with history of hypersensitivity to fingolimod or any of its excipients [see Contraindications (4)].

6 ADVERSE REACTIONS

The following serious adverse reactions are described elsewhere in labeling:

- Bradyarrhythmia and Atrioventricular Blocks [see Warnings and Precautions (5.1)]
- Infections [see Warnings and Precautions (5.2)]
- Progressive Multifocal Leukoencephalopathy [see Warnings and Precautions (5.3)]
- Macular Edema [see Warnings and Precautions (5.4)]
- Liver Injury [see Warnings and Precautions (5.5)]
- Posterior Reversible Encephalopathy Syndrome [see Warnings and Precautions (5.6)]
- Respiratory Effects [see Warnings and Precautions (5.7)]
- Fetal Risk [see Warnings and Precautions (5.8)]
- Severe Increase in Disability After Stopping TASCENSO ODT [see Warnings and Precautions (5.9)]
- Tumefactive Multiple Sclerosis [see Warnings and Precautions (5.10)]
- Increased Blood Pressure [see Warnings and Precautions (5.11)]
- Malignancies [see Warnings and Precautions (5.12)]
- Immune System Effects Following TASCENSO ODT Discontinuation [see Warnings and Precautions (5.13)]
- Hypersensitivity Reactions [see Warnings and Precautions (5.14)]

6.1 Clinical Trials Experience

Because clinical trials are conducted under widely varying conditions, adverse reaction rates observed in the clinical trials of a drug cannot be directly compared to rates in the clinical trials of another drug and may not reflect the rates observed in practice.

Adults

In clinical trials (Studies 1, 2, and 3), a total of 1212 patients with relapsing forms of multiple sclerosis received fingolimod 0.5 mg capsules. This included 783 patients who received fingolimod 0.5 mg in the 2-year placebo-controlled trials (Studies 1 and 3) and 429 patients who received fingolimod 0.5 mg in the 1-year active-controlled trial (Study 2). The overall exposure in the controlled trials was equivalent to 1716 person-years. Approximately 1000 patients received at least 2 years of treatment with fingolimod 0.5 mg capsules. In all clinical studies, including uncontrolled extension studies, the exposure to fingolimod 0.5 mg capsules was approximately 4119 person-years.

In placebo-controlled trials, the most frequent adverse reactions (incidence ≥ 10% and greater than placebo) for fingolimod 0.5 mg capsules were headache, liver transaminase elevation, diarrhea, cough, influenza, sinusitis, back pain, abdominal pain, and pain in extremity. Adverse events that led to treatment discontinuation and occurred in more than 1% of patients taking fingolimod 0.5 mg capsules, were serum transaminase elevations (4.7% compared to 1% on placebo) and basal cell carcinoma (1% compared to 0.5% on placebo).

Table 1 lists adverse reactions in clinical studies in adults that occurred in ≥ 1% of fingolimod-treated patients and ≥ 1% higher rate than for placebo.

Table 1: Adverse Reactions Reported in Adult Studies 1 and 3 (Occurring in ≥ 1% of Patients and Reported for Fingolimod 0.5 mg Capsules at ≥ 1% Higher Rate than for Placebo)
 | Fingolimod 0.5 mg Capsules N = 783 | Placebo N = 773
Adverse Drug Reactions | % | %
Infections
Influenza | 11 | 8
Sinusitis | 11 | 8
Bronchitis | 8 | 5
Herpes zoster | 2 | 1
Tinea versicolor | 2 | < 1
Cardiac disorders
Bradycardia | 3 | 1
Nervous system disorders
Headache | 25 | 24
Migraine | 6 | 4
Gastrointestinal disorders
Nausea | 13 | 12
Diarrhea | 13 | 10
Abdominal pain | 11 | 10
General disorders and administration-site conditions
Asthenia | 2 | 1
Musculoskeletal and connective tissue disorders
Back pain | 10 | 9
Pain in extremity | 10 | 7
Skin and subcutaneous tissue disorders
Alopecia | 3 | 2
Actinic keratosis | 2 | 1
Investigations
Liver transaminase elevations (ALT/GGT/AST) | 15 | 4
Blood triglycerides increased | 3 | 1
Respiratory, thoracic, and mediastinal disorders
Cough | 12 | 11
Dyspnea | 9 | 7
Eye disorders
Vision blurred | 4 | 2
Vascular disorders
Hypertension | 8 | 4
Blood and lymphatic system disorders
Lymphopenia | 7 | < 1
Leukopenia | 2 | < 1
Neoplasms benign, malignant, and unspecified (including cysts and polyps)
Skin papilloma | 3 | 2
Basal cell carcinoma | 2 | 1

Abbreviations: ALT, alanine transaminase; AST, aspartate transferase; GGT, gamma-glutamyl transferase.

Adverse reactions of seizure, dizziness, pneumonia, eczema, and pruritus were also reported in Studies 1 and 3 but did not meet the reporting rate criteria for inclusion in Table 1 (difference was less than 1%).

Adverse reactions with fingolimod 0.5 mg in Study 2, the 1-year active-controlled (versus interferon beta-1a) study were generally similar to those in Studies 1 and 3.

Vascular Events

Vascular events, including ischemic and hemorrhagic strokes, and peripheral arterial occlusive disease were reported in premarketing clinical trials in patients who received fingolimod doses (1.25 mg to 5 mg) higher than recommended for use in MS. Similar events have been reported with fingolimod treatment in the postmarketing setting although a causal relationship has not been established.

Seizure

Cases of seizures, including status epilepticus, have been reported with the use of fingolimod capsules in clinical trials and in the postmarketing setting in adults [see Adverse Reactions (6.2)]. In adult clinical trials, the rate of seizures was 0.9% in fingolimod - treated patients and 0.3% in placebo-treated patients. It is unknown whether these events were related to the effects of multiple sclerosis alone, to fingolimod, or to a combination of both.

Pediatric Patients 10 Years of Age and Older

In the controlled pediatric trial (Study 4), the safety profile in pediatric patients receiving fingolimod 0.25 mg or 0.5 mg capsules daily was similar to that seen in adult patients.

In the pediatric study, cases of seizures were reported in 5.6% of fingolimod-treated patients and 0.9% of interferon beta-1a-treated patients [see Use in Specific Populations (8.4)].

6.2 Postmarketing Experience

The following adverse reactions have been identified during postapproval use of fingolimod. Because these reactions are reported voluntarily from a population of uncertain size, it is not always possible to reliably estimate their frequency or establish a causal relationship to drug exposure.

Blood and Lymphatic System Disorders: Hemolytic anemia and thrombocytopenia

Hepatobiliary Disorders: Liver injury [see Warnings and Precautions (5.5)]

Infections: Infections including cryptococcal infections [see Warnings and Precautions (5.2)], human papilloma virus (HPV) infection, including papilloma, dysplasia, warts and HPV-related cancer [see Warnings and Precautions (5.2)], progressive multifocal leukoencephalopathy [see Warnings and Precautions (5.3)]

Musculoskeletal and connective tissue disorders: Arthralgia, myalgia

Nervous System Disorders: Posterior reversible encephalopathy syndrome [see Warnings and Precautions (5.6)], seizures, including status epilepticus [see Adverse Reactions (6.1)]

Neoplasms, Benign, Malignant, and Unspecified (including cysts and polyps): melanoma, Merkel cell carcinoma, cutaneous T- cell lymphoma (including mycosis fungoides), Kaposi’s sarcoma and, squamous cell carcinoma [see Warnings and Precautions (5.12)]

Skin and Subcutaneous Tissue Disorders: Hypersensitivity [see Warnings and Precautions (5.14)]

7 DRUG INTERACTIONS

7.1 QT Prolonging Drugs

TASCENSO ODT has not been studied in patients treated with drugs that prolong the QT interval. Drugs that prolong the QT interval have been associated with cases of torsades de pointes in patients with bradycardia. Since initiation of TASCENSO ODT treatment results in decreased heart rate and may prolong the QT interval, patients on QT prolonging drugs with a known risk of torsades de pointes (e.g., citalopram, chlorpromazine, haloperidol, methadone, erythromycin) should be monitored overnight with continuous ECG in a medical facility [see Dosage and Administration (2.4), Warnings and Precautions (5.1)].

7.2 Ketoconazole

The blood levels of fingolimod and fingolimod-phosphate are increased by 1.7-fold when used concomitantly with ketoconazole. Patients who use TASCENSO ODT and systemic ketoconazole concomitantly should be closely monitored, as the risk of adverse reactions is greater.

7.3 Vaccines

TASCENSO ODT reduces the immune response to vaccination. Vaccination may be less effective during and for up to 2 months after discontinuation of treatment with TASCENSO ODT [see Clinical Pharmacology (12.2)]. Avoid the use of live attenuated vaccines during and for 2 months after treatment with TASCENSO ODT because of the risk of infection.

It is recommended that pediatric patients, if possible, be brought up to date with all immunizations in agreement with current immunization guidelines prior to initiating TASCENSO ODT therapy.

7.4 Antineoplastic, Immunosuppressive, or Immune-Modulating Therapies

Antineoplastic, immune-modulating, or immunosuppressive therapies, (including corticosteroids) are expected to increase the risk of immunosuppression, and the risk of additive immune system effects must be considered if these therapies are coadministered with TASCENSO ODT. When switching from drugs with prolonged immune effects, such as natalizumab, teriflunomide or mitoxantrone, the duration and mode of action of these drugs must be considered to avoid unintended additive immunosuppressive effects when initiating TASCENSO ODT [see Warnings and Precautions (5.2)].

7.5 Drugs That Slow Heart Rate or Atrioventricular Conduction (e.g., beta blockers or diltiazem)

Experience with fingolimod in patients receiving concurrent therapy with drugs that slow the heart rate or AV conduction (e.g., beta blockers, digoxin, or heart rate-slowing calcium channel blockers such as diltiazem or verapamil) is limited. Because initiation of TASCENSO ODT treatment may result in an additional decrease in heart rate, concomitant use of these drugs during TASCENSO ODT initiation may be associated with severe bradycardia or heart block. Seek advice from the physician prescribing these drugs regarding the possibility to switch to drugs that do not slow the heart rate or atrioventricular conduction before initiating TASCENSO ODT. Patients who cannot switch should have overnight continuous ECG monitoring after the first dose [see Dosage and Administration (2.4), Warnings and Precautions (5.1)].

7.6 Laboratory Test Interaction

Because fingolimod reduces blood lymphocyte counts via redistribution in secondary lymphoid organs, peripheral blood lymphocyte counts cannot be utilized to evaluate the lymphocyte subset status of a patient treated with fingolimod. A recent CBC should be available before initiating treatment with TASCENSO ODT.

8 USE IN SPECIFIC POPULATIONS

8.1 Pregnancy

Risk Summary

Based on findings from animal studies, TASCENSO ODT may cause fetal harm when administered to a pregnant woman. Data from prospective reports to the fingolimod pregnancy registry are currently not sufficient to allow for an adequate assessment of the drug-associated risk for birth defects and miscarriage in humans.

In oral studies conducted in rats and rabbits, fingolimod demonstrated developmental toxicity, including an increase in malformations (rats) and embryolethality, when given to pregnant animals. In rats, the highest no-effect dose was less than the recommended human dose of 0.5 mg/day on a body surface area (mg/m^2) basis. The most common fetal visceral malformations in rats were persistent truncus arteriosus and ventricular septal defect. The receptor affected by fingolimod (sphingosine 1-phosphate receptor) is known to be involved in vascular formation during embryogenesis (see Data). Advise pregnant women of the potential risk to a fetus.

In the US general population, the estimated background risk of major birth defects and miscarriage in clinically recognized pregnancies is 2%-4% and 15%-20%, respectively. The background risk of major birth defects and miscarriage for the indicated population is unknown.

Clinical Considerations

In females planning to become pregnant, TASCENSO ODT should be stopped 2 months before planned conception.

The possibility of severe increase in disability should be considered in women who discontinue or are considering discontinuation of TASCENSO ODT because of pregnancy or planned pregnancy. In many of the cases in which increase in disability was reported after stopping fingolimod, the active moiety in TASCENSO ODT, patients had stopped fingolimod because of pregnancy or planned pregnancy [see Warnings and Precautions (5.9].

Data

Animal Data

When fingolimod was orally administered to pregnant rats during the period of organogenesis (0, 0.03, 0.1, and 0.3 mg/kg/day or 0, 1, 3, and 10 mg/kg/day), increased incidences of fetal malformations and embryofetal deaths were observed at all but the lowest dose tested (0.03 mg/kg/day), which is less than the recommended human dose (RHD) on a mg/m^2 basis. Oral administration to pregnant rabbits during organogenesis (0, 0.5, 1.5, and 5 mg/kg/day) resulted in increased incidences of embryofetal mortality and fetal growth retardation at the mid and high doses. The no-effect dose for these effects in rabbits (0.5 mg/kg/day) is approximately 20 times the RHD on a mg/m^2 basis.

When fingolimod was orally administered to female rats during pregnancy and lactation (0, 0.05, 0.15, and 0.5 mg/kg/day), pup survival was decreased at all doses and a neurobehavioral (learning) deficit was seen in offspring at the high dose. The low-effect dose of 0.05 mg/kg/day is similar to the RHD on a mg/m^2 basis.

8.2 Lactation

Risk Summary

There are no data on the presence of fingolimod in human milk, the effects on the breastfed infant, or the effects of the drug on milk production. Fingolimod is excreted in the milk of treated rats. When a drug is present in animal milk, it is likely that the drug will be present in human milk. The developmental and health benefits of breastfeeding should be considered along with the mother's clinical need for TASCENSO ODT and any potential adverse effects on the breastfed infant from TASCENSO ODT or from the underlying maternal condition.

8.3 Females and Males of Reproductive Potential

Pregnancy Testing

The pregnancy status of females of reproductive potential should be verified prior to starting treatment with TASCENSO ODT [see Use in Specific Populations (8.1)].

Contraception

Before initiation of TASCENSO ODT, females of reproductive potential should be counseled on the potential for a serious risk to the fetus and the need for effective contraception during treatment with TASCENSO ODT [see Warnings and Precautions (5.9) and Use in Specific Populations (8.1)]. Since it takes approximately 2 months to eliminate the compound from the body after stopping treatment, the potential risk to the fetus may persist and women should use effective contraception during this period [see Warnings and Precautions (5.8, 5.13)].

8.4 Pediatric Use

Safety and effectiveness of fingolimod for the treatment of relapsing forms of multiple sclerosis in pediatric patients 10 to less than 18 years of age were established in one randomized, double-blind clinical study in 215 patients (fingolimod n = 107; intramuscular interferon (IFN) beta-1a n = 108) [see Clinical Studies (14.2)].

In the controlled pediatric study, the safety profile in pediatric patients (10 to less than 18 years of age) receiving fingolimod 0.25 mg or 0.5 mg capsules daily was similar to that seen in adult patients. In the pediatric study, cases of seizures were reported in 5.6% of fingolimod-treated patients and 0.9% of interferon beta-1a-treated patients.

It is recommended that pediatric patients, if possible, complete all immunizations in accordance with current immunization guidelines prior to initiating TASCENSO ODT therapy.

Safety and effectiveness of TASCENSO ODT in pediatric patients below the age of 10 years have not been established.

Juvenile Animal Toxicity Data

In a study in which fingolimod (0.3, 1.5, or 7.5 mg/kg/day) was orally administered to young rats from weaning through sexual maturity, changes in bone mineral density and persistent neurobehavioral impairment (altered auditory startle) were observed at all doses. Delayed sexual maturation was noted in females at the highest dose tested and in males at all doses. The bone changes observed in fingolimod-treated juvenile rats are consistent with a reported role of S1P in the regulation of bone mineral homeostasis.

When fingolimod (0.5 or 5 mg/kg/day) was orally administered to rats from the neonatal period through sexual maturity, a marked decrease in T-cell dependent antibody response was observed at both doses. This effect had not fully recovered by 6 to 8 weeks after the end of treatment.

Overall, a no-effect dose for adverse developmental effects in juvenile animals was not identified.

8.5 Geriatric Use

Clinical MS studies of fingolimod capsules did not include sufficient numbers of patients aged 65 years and over to determine whether they respond differently than younger patients. TASCENSO ODT should be used with caution in patients aged 65 years and over, reflecting the greater frequency of decreased hepatic, or renal, function and of concomitant disease or other drug therapy.

8.6 Hepatic Impairment

Because fingolimod, but not fingolimod-phosphate, exposure is doubled in patients with severe hepatic impairment, patients with severe hepatic impairment should be closely monitored, as the risk of adverse reactions may be greater [see Warnings and Precautions (5.6), Clinical Pharmacology (12.3)].

No dose adjustment is needed in patients with mild or moderate hepatic impairment.

8.7 Renal Impairment

The blood level of some fingolimod metabolites is increased (up to 13-fold) in patients with severe renal impairment [see Clinical Pharmacology (12.3)]. The toxicity of these metabolites has not been fully explored. The blood level of these metabolites has not been assessed in patients with mild or moderate renal impairment.

10 OVERDOSAGE

Fingolimod, the active moiety in TASCENSO ODT, can induce bradycardia as well as AV conduction blocks (including complete AV block). The decline in heart rate usually starts within 1 hour of the first dose and is maximal within 6 hours in most patients [see Warnings and Precautions (5.1)]. In case of TASCENSO ODT overdosage, observe patients overnight with continuous ECG monitoring in a medical facility, and obtain regular measurements of blood pressure. [see Dosage and Administration (2.4)].

Neither dialysis nor plasma exchange results in removal of fingolimod from the body.

11 DESCRIPTION

Fingolimod is a sphingosine 1-phosphate receptor modulator.

Chemically, fingolimod lauryl sulfate is 2-amino-2-[2-(4-octylphenyl)ethyl]propan-1,3-diol lauryl sulfate. Its structure is shown below:

Fingolimod lauryl sulfate is a white to practically white powder that is practically insoluble in water. It has a molecular weight of 573.87 g/mol.

TASCENSO ODT is provided as 0.25 mg and 0.5 mg orally disintegrating tablets for oral use.

Each orally disintegrating tablet contains 0.25 mg or 0.5 mg of fingolimod (equivalent to 0.47 mg or 0.93 mg of fingolimod lauryl sulfate) and the following inactive ingredients: gelatin, mannitol, medium-chain triglycerides, sodium chloride, and sodium lauryl sulfate.

12 CLINICAL PHARMACOLOGY

12.1 Mechanism of Action

Fingolimod is metabolized by sphingosine kinase to the active metabolite, fingolimod-phosphate. Fingolimod phosphate is a sphingosine 1-phosphate receptor modulator and binds with high affinity to sphingosine 1-phosphate receptors 1, 3, 4, and 5. Fingolimod-phosphate blocks the capacity of lymphocytes to egress from lymph nodes, reducing the number of lymphocytes in peripheral blood. The mechanism by which fingolimod exerts therapeutic effects in multiple sclerosis is unknown but may involve reduction of lymphocyte migration into the central nervous system.

12.2 Pharmacodynamics

Heart Rate and Rhythm

Fingolimod causes a transient reduction in heart rate and AV conduction at treatment initiation [see Warnings and Precautions (5.1)].

Heart rate progressively increases after the first day, returning to baseline values within 1 month of the start of chronic treatment.

Autonomic responses of the heart, including diurnal variation of heart rate and response to exercise, are not affected by fingolimod treatment.

Fingolimod treatment is not associated with a decrease in cardiac output.

Potential to Prolong the QT Interval

In a thorough QT interval study of doses of 1.25 or 2.5 mg fingolimod capsules at steady-state, when a negative chronotropic effect of fingolimod was still present, fingolimod treatment resulted in a prolongation of QTc, with the upper boundary of the 90% confidence interval (CI) of 14.0 msec. There is no consistent signal of increased incidence of QTc outliers, either absolute or change from baseline, associated with fingolimod treatment. In MS studies, there was no clinically relevant prolongation of the QT interval, but patients at risk for QT prolongation were not included in clinical studies.

Immune System

Effects on Immune Cell Numbers in the Blood

In a study in which 12 adult subjects received fingolimod 0.5 mg capsules daily, the lymphocyte count decreased to approximately 60% of baseline within 4 to 6 hours after the first dose. With continued daily dosing, the lymphocyte count continued to decrease over a 2-week period, reaching a nadir count of approximately 500 cells/mcL or approximately 30% of baseline. In a placebo-controlled study in 1272 MS patients (of whom 425 received fingolimod 0.5 mg capsules daily and 418 received placebo), 18% (N = 78) of patients on fingolimod 0.5 mg reached a nadir of < 200 cells/mcL on at least 1 occasion. No patient on placebo reached a nadir of < 200 cells/mcL. Low lymphocyte counts are maintained with chronic daily dosing of fingolimod 0.5 mg daily.

Chronic fingolimod dosing leads to a mild decrease in the neutrophil count to approximately 80% of baseline. Monocytes are unaffected by fingolimod.

Peripheral lymphocyte count increases are evident within days of stopping fingolimod treatment and typically normal counts are reached within 1 to 2 months.

Effect on Antibody Response

Fingolimod reduces the immune response to vaccination, as evaluated in 2 studies.

In the first study, the immunogenicity of keyhole limpet hemocyanin (KLH) and pneumococcal polysaccharide vaccine (PPV-23) immunization were assessed by IgM and IgG titers in a steady-state, randomized, placebo-controlled study in healthy adult volunteers. Compared to placebo, antigen-specific IgM titers were decreased by 91% and 25% in response to KLH and PPV-23, respectively, in subjects on fingolimod 0.5 mg capsules. Similarly, IgG titers were decreased by 45% and 50%, in response to KLH and PPV-23, respectively, in subjects on fingolimod 0.5 mg daily compared to placebo. The responder rate for fingolimod 0.5 mg as measured by the number of subjects with a > 4-fold increase in KLH IgG was comparable to placebo and 25% lower for PPV-23 IgG, while the number of subjects with a > 4-fold increase in KLH and PPV-23 IgM was 75% and 40% lower, respectively, compared to placebo. The capacity to mount a skin delayed-type hypersensitivity reaction to Candida and tetanus toxoid was decreased by approximately 30% in subjects on fingolimod 0.5 mg daily, compared to placebo. Immunologic responses were further decreased with fingolimod 1.25 mg (a dose higher than recommended in MS) [see Warnings and Precautions (5.2)].

In the second study, the immunogenicity of Northern hemisphere seasonal influenza and tetanus toxoid vaccination was assessed in a 12-week steady-state, randomized, placebo-controlled study of fingolimod 0.5 mg capsules in adult multiple sclerosis patients (n = 136). The responder rate 3 weeks after vaccination, defined as seroconversion or a ≥ 4-fold increase in antibody directed against at least 1 of the 3 influenza strains, was 54% for fingolimod 0.5 mg and 85% in the placebo group. The responder rate 3 weeks after vaccination, defined as seroconversion or a ≥ 4-fold increase in antibody directed against tetanus toxoid was 40% for fingolimod 0.5 mg and 61% in the placebo group.

Pulmonary Function

Single fingolimod doses ≥ 5 mg (10-fold the recommended dose) are associated with a dose-dependent increase in airway resistance. In a 14-day study of 0.5, 1.25, or 5 mg/day, fingolimod was not associated with impaired oxygenation or oxygen desaturation with exercise or an increase in airway responsiveness to methacholine. Subjects on fingolimod treatment had a normal bronchodilator response to inhaled beta-agonists.

In a 14-day placebo-controlled study of adult patients with moderate asthma, no effect was seen for fingolimod 0.5 mg capsules (recommended dose in MS). A 10% reduction in mean FEV1 at 6 hours after dosing was observed in adult patients receiving fingolimod 1.25 mg (a dose higher than recommended for use in MS) on Day 10 of treatment. Fingolimod 1.25 mg was associated with a 5-fold increase in the use of rescue short-acting beta-agonists.

12.3 Pharmacokinetics

Absorption

The Tmax of fingolimod is 12 to 16 hours. The apparent absolute oral bioavailability is 93%.

Food intake does not alter Cmax or (AUC) of fingolimod or fingolimod-phosphate. Therefore, TASCENSO ODT may be taken without regard to meals.

Steady-state blood concentrations of fingolimod are reached within 1 to 2 months following once-daily administration and steady-state levels are approximately 10-fold greater than with the initial dose.

Distribution

Fingolimod highly (86%) distributes in red blood cells. Fingolimod-phosphate has a smaller uptake in blood cells of < 17%. Fingolimod and fingolimod-phosphate are > 99.7% protein bound. Fingolimod and fingolimod-phosphate protein binding is not altered by renal or hepatic impairment.

Fingolimod is extensively distributed to body tissues with a volume of distribution of about 1200 ± 260 L.

Metabolism

The biotransformation of fingolimod in humans occurs by 3 main pathways: by reversible stereoselective phosphorylation to the pharmacologically active (S)-enantiomer of fingolimod-phosphate, by oxidative biotransformation catalyzed mainly by the cytochrome P450 4F2 (CYP4F2) and possibly other CYP4F isoenzymes with subsequent fatty acid-like degradation to inactive metabolites, and by formation of pharmacologically inactive non-polar ceramide analogs of fingolimod.

Inhibitors or inducers of CYP4F2 and possibly other CYP4F isozymes might alter the exposure of fingolimod or fingolimod-phosphate. In vitro studies in hepatocytes indicated that CYP3A4 may contribute to fingolimod metabolism in the case of strong induction of CYP3A4.

Following single oral administration of [^14C] fingolimod, the major fingolimod-related components in blood, as judged from their contribution to the AUC up to 816 hours post-dose of total radiolabeled components, are fingolimod itself (23.3%), fingolimod-phosphate (10.3%), and inactive metabolites [M3 carboxylic acid metabolite (8.3%), M29 ceramide metabolite (8.9%), and M30 ceramide metabolite (7.3%)].

Elimination

Fingolimod blood clearance is 6.3 ± 2.3 L/h, and the average apparent terminal half-life (t1/2) is 6 to 9 days. Blood levels of fingolimod-phosphate decline in parallel with those of fingolimod in the terminal phase, yielding similar half-lives for both.

After oral administration, about 81% of the dose is slowly excreted in the urine as inactive metabolites. Fingolimod and fingolimod-phosphate are not excreted intact in urine but are the major components in the feces with amounts of each representing less than 2.5% of the dose.

Specific Populations

Pediatric Patients

The median fingolimod-phosphate (fingolimod-P) concentration in pediatric MS patients aged 10 to less than 18 years was 1.10 ng/mL, as compared to 1.35 ng/mL in adult MS patients.

Geriatric Patients
The mechanism for elimination and results from population pharmacokinetics suggest that dose adjustment would not be necessary in elderly patients. However, clinical experience in patients aged above 65 years is limited.

Gender

Gender has no clinically significant influence on fingolimod and fingolimod-phosphate pharmacokinetics.

Race

The effects of race on fingolimod and fingolimod-phosphate pharmacokinetics cannot be adequately assessed due to a low number of patients who self-identified as Black or African American, Asian, or other races in the clinical program.

Renal Impairment

In adult patients with severe renal impairment, fingolimod Cmax and AUC are increased by 32% and 43%, respectively, and fingolimod-phosphate Cmax and AUC are increased by 25% and 14%, respectively, with no change in apparent elimination half-life. Based on these findings, the TASCENSO ODT 0.5 mg dose is appropriate for use in adult patients with renal impairment. TASCENSO ODT 0.25 mg and 0.5 mg are appropriate for use in pediatric patients with renal impairment. The systemic exposure of 2 metabolites (M2 and M3) is increased by 3-and 13-fold, respectively. The toxicity of these metabolites has not been fully characterized.

A study in patients with mild or moderate renal impairment has not been conducted.

Hepatic Impairment

In subjects with mild, moderate, or severe hepatic impairment (Child-Pugh class A, B, and C), no change in fingolimod Cmax was observed, but fingolimod AUC0-∞ was increased respectively by 12%, 44%, and 103%. In patients with severe hepatic impairment (Child-Pugh class C), fingolimod-phosphate Cmax was decreased by 22% and AUC0-96 hours was decreased by 29%. The pharmacokinetics of fingolimod-phosphate was not evaluated in patients with mild or moderate hepatic impairment. The apparent elimination half-life of fingolimod is unchanged in subjects with mild hepatic impairment but is prolonged by about 50% in patients with moderate or severe hepatic impairment.

Patients with severe hepatic impairment (Child-Pugh class C) should be closely monitored, as the risk of adverse reactions is greater [see Warnings and Precautions (5.6)].

No dose adjustment is needed in patients with mild or moderate hepatic impairment (Child-Pugh class A and B).

Drug Interactions

Ketoconazole

The coadministration of ketoconazole (a potent inhibitor of CYP3A and CYP4F) 200 mg twice-daily at steady-state and a single dose of fingolimod 5 mg led to a 70% increase in AUC of fingolimod and fingolimod-phosphate. Patients who use TASCENSO ODT and systemic ketoconazole concomitantly should be closely monitored, as the risk of adverse reactions is greater [see Drug Interactions (7.2)].

Carbamazepine

The coadministration of carbamazepine (a potent CYP450 enzyme inducer) 600 mg twice-daily at steady-state and a single dose of fingolimod 2 mg decreased blood concentrations (AUC) of fingolimod and fingolimod-phosphate by approximately 40%. The clinical impact of this decrease is unknown.

Other strong CYP450 enzyme inducers, e.g., rifampicin, phenytoin, phenobarbital, and St. John's wort, may also reduce AUC of fingolimod and fingolimod-phosphate. The clinical impact of this potential decrease is unknown.

Potential of Fingolimod and Fingolimod-phosphate to Inhibit the Metabolism of Comedications

In vitro inhibition studies using pooled human liver microsomes and specific metabolic probe substrates demonstrate that fingolimod has little or no capacity to inhibit the activity of the following CYP enzymes: CYP1A2, CYP2A6, CYP2B6, CYP2C8, CYP2C9, CYP2C19, CYP2D6, CYP2E1, CYP3A4/5, or CYP4A9/11 (fingolimod only), and similarly fingolimod-phosphate has little or no capacity to inhibit the activity of CYP1A2, CYP2A6, CYP2B6, CYP2C8, CYP2C9, CYP2C19, CYP2D6, CYP2E1, or CYP3A4 at concentrations up to 3 orders of magnitude of therapeutic concentrations. Therefore, fingolimod and fingolimod-phosphate are unlikely to reduce the clearance of drugs that are mainly cleared through metabolism by the major CYP isoenzymes described above.

Potential of Fingolimod and Fingolimod-phosphate to Induce its Own and/or the Metabolism of Comedications

Fingolimod was examined for its potential to induce human CYP3A4, CYP1A2, CYP4F2, and MDR1 (P-glycoprotein) mRNA and CYP3A, CYP1A2, CYP2B6, CYP2C8, CYP2C9, CYP2C19, and CYP4F2 activity in primary human hepatocytes. Fingolimod did not induce mRNA or activity of the different CYP enzymes and MDR1 with respect to the vehicle control; therefore, no clinically relevant induction of the tested CYP enzymes or MDR1 by fingolimod are expected at therapeutic concentrations. Fingolimod-phosphate was also examined for its potential to induce mRNA and/or activity of human CYP1A2, CYP2B6, CYP2C8, CYP2C9, CYP2C19, CYP3A, CYP4F2, CYP4F3B, and CYP4F12. Fingolimod-phosphate is not expected to have clinically significant induction effects on these enzymes at therapeutic doses of fingolimod. In vitro experiments did not provide an indication of CYP induction by fingolimod-phosphate.

Transporters

Based on in vitro data, fingolimod as well as fingolimod-phosphate are not expected to inhibit the uptake of comedications and/or biologics transported by the organic anion transporting polypeptides OATP1B1, OATP1B3, or the sodium taurocholate co-transporting polypeptide (NTCP). Similarly, they are not expected to inhibit the efflux of comedications and/or biologics transported by the breast cancer resistance protein (BCRP), the bile salt export pump (BSEP), the multidrug resistance-associated protein 2 (MRP2), or P-glycoprotein (P-gp) at therapeutic concentrations.

Oral Contraceptives

The coadministration of fingolimod 0.5 mg capsules daily with oral contraceptives (ethinylestradiol and levonorgestrel) did not elicit any clinically significant change in oral contraceptives exposure. Fingolimod and fingolimod-phosphate exposure were consistent with those from previous studies. No interaction studies have been performed with oral contraceptives containing other progestagens; however, an effect of fingolimod on their exposure is not expected.

Cyclosporine

The pharmacokinetics of single-dose fingolimod was not altered during coadministration with cyclosporine at steady-state, nor was cyclosporine steady-state pharmacokinetics altered by fingolimod. These data indicate that TASCENSO ODT is unlikely to reduce or increase the clearance of drugs cleared mainly by CYP3A4. Potent inhibition of transporters MDR1 (P-gp), MRP2, and OATP-1B1 does not influence fingolimod disposition.

Isoproterenol, Atropine, Atenolol, and Diltiazem

Single-dose fingolimod and fingolimod-phosphate exposure was not altered by coadministered isoproterenol or atropine. Likewise, the single-dose pharmacokinetics of fingolimod and fingolimod-phosphate and the steady-state pharmacokinetics of both atenolol and diltiazem were unchanged during the coadministration of the latter 2 drugs individually with fingolimod.

Population Pharmacokinetics Analysis

A population pharmacokinetics evaluation performed in MS patients did not provide evidence for a significant effect of fluoxetine and paroxetine (strong CYP2D6 inhibitors) on fingolimod or fingolimod-phosphate predose concentrations. In addition, the following commonly coprescribed substances had no clinically relevant effect (< 20%) on fingolimod or fingolimod-phosphate predose concentrations: baclofen, gabapentin, oxybutynin, amantadine, modafinil, amitriptyline, pregabalin, and corticosteroids.

13 NONCLINICAL TOXICOLOGY

13.1 Carcinogenesis, Mutagenesis, Impairment of Fertility

Oral carcinogenicity studies of fingolimod were conducted in mice and rats. In mice, fingolimod was administered at oral doses of 0, 0.025, 0.25, and 2.5 mg/kg/day for up to 2 years. The incidence of malignant lymphoma was increased in males and females at the mid and high dose. The lowest dose tested (0.025 mg/kg/day) is less than the RHD of 0.5 mg/day on a body surface area (mg/m^2) basis. In rats, fingolimod was administered at oral doses of 0, 0.05, 0.15, 0.5, and 2.5 mg/kg/day. No increase in tumors was observed. The highest dose tested (2.5 mg/kg/day) is approximately 50 times the RHD on a mg/m^2 basis.

Fingolimod was negative in a battery of in vitro (Ames, mouse lymphoma thymidine kinase, chromosomal aberration in mammalian cells) and in vivo (micronucleus in mouse and rat) assays.

When fingolimod was administered orally (0, 1, 3, and 10 mg/kg/day) to male and female rats prior to and during mating, and continuing to Day 7 of gestation in females, no effect on fertility was observed up to the highest dose tested (10 mg/kg), which is approximately 200 times the RHD on a mg/m^2 basis.

13.2 Animal Toxicology and/or Pharmacology

Lung toxicity was observed in 2 different strains of rats and in dogs and monkeys. The primary findings included increase in lung weight, associated with smooth muscle hypertrophy, hyperdistention of the alveoli, and/or increased collagen. Insufficient or lack of pulmonary collapse at necropsy, generally correlated with microscopic changes, was observed in all species. In rats and monkeys, lung toxicity was observed at all oral doses tested in chronic studies. The lowest doses tested in rats (0.05 mg/kg/day in the 2-year carcinogenicity study) and monkeys (0.5 mg/kg/day in the 39-week toxicity study) are similar to and approximately 20 times the RHD on a mg/m^2 basis, respectively.

In the 52-week oral study in monkeys, respiratory distress associated with ketamine administration was observed at doses of 3 and 10 mg/kg/day; the most affected animal became hypoxic and required oxygenation. As ketamine is not generally associated with respiratory depression, this effect was attributed to fingolimod. In a subsequent study in rats, ketamine was shown to potentiate the bronchoconstrictive effects of fingolimod. The relevance of these findings to humans is unknown.

14 CLINICAL STUDIES

The efficacy of TASCENSO ODT is based on the relative bioavailability of TASCENSO ODT orally disintegrating tablets compared to fingolimod capsules in healthy adults [see Clinical Pharmacology (12.3)].

The clinical studies described below were conducted using fingolimod capsules.

14.1 Adults

The efficacy of fingolimod was demonstrated in 2 studies that evaluated once-daily doses of fingolimod capsules 0.5 mg and 1.25 mg in patients with relapsing-remitting MS (RRMS). Both studies included patients who had experienced at least 2 clinical relapses during the 2 years prior to randomization or at least 1 clinical relapse during the 1 year prior to randomization and had an Expanded Disability Status Scale (EDSS) score from 0 to 5.5. Study 1 was a 2-year randomized, double-blind, placebo-controlled study in patients with RRMS who had not received any interferon-beta or glatiramer acetate for at least the previous 3 months and had not received any natalizumab for at least the previous 6 months. Neurological evaluations were performed at screening, every 3 months and at time of suspected relapse. MRI evaluations were performed at screening, Month 6, Month 12, and Month 24. The primary endpoint was the annualized relapse rate.

Median age was 37 years, median disease duration was 6.7 years and median EDSS score at baseline was 2.0. Patients were randomized to receive fingolimod 0.5 mg (N = 425), 1.25 mg (N = 429), or placebo (N = 418) for up to 24 months. Median time on study drug was 717 days on 0.5 mg, 715 days on 1.25 mg, and 719 days on placebo.

The annualized relapse rate was significantly lower in patients treated with fingolimod than in patients who received placebo. The secondary endpoint was the time to 3-month confirmed disability progression as measured by at least a 1-point increase from baseline in EDSS (0.5-point increase for patients with baseline EDSS of 5.5) sustained for 3 months. Time to onset of 3-month confirmed disability progression was significantly delayed with fingolimod treatment compared to placebo. The 1.25 mg dose resulted in no additional benefit over the fingolimod 0.5 mg dose. The results for this study are shown in Table 2 and Figure 1.

Table 2: Clinical and MRI Results of Study 1
 | Fingolimod Capsules 0.5 mg | Placebo | p-value
 | N = 425 | N = 418
Clinical Endpoints
Annualized relapse rate (primary endpoint) | 0.18 | 0.40 | < 0.001
Percentage of patients without relapse | 70% | 46% | < 0.001
Hazard ratio§ of disability progression (95% CI) | 0.70 (0.52, 0.96) |  | 0.02
MRI Endpoint
Mean (median) number of new or newly enlarging T2 lesions over 24 months | 2.5 (0) | 9.8 (5.0) | < 0.001
Mean (median) number of T1 Gd-enhancing lesions at Month 24 | 0.2 (0) | 1.1 (0) | < 0.001

Abbreviation: CI, confidence interval.

All analyses of clinical endpoints were intent-to-treat. MRI analysis used evaluable dataset.
§Hazard ratio is an estimate of the relative risk of having the event of disability progression on fingolimod as compared to placebo.

Figure 1: Time to 3-Month Confirmed Disability Progression - Study 1 (ITT population)

Study 2 was a 1-year randomized, double-blind, double-dummy, active-controlled study in patients with RRMS who had not received any natalizumab in the previous 6 months. Prior therapy with interferon-beta or glatiramer acetate up to the time of randomization was permitted.

Neurological evaluations were performed at screening, every 3 months, and at the time of suspected relapses. MRI evaluations were performed at screening and at Month 12. The primary endpoint was the annualized relapse rate.

Median age was 36 years, median disease duration was 5.9 years, and median EDSS score at baseline was 2.0. Patients were randomized to receive fingolimod capsules 0.5 mg (N = 431), 1.25 mg (N = 426), or interferon beta-1a, 30 mcg via the intramuscular route (IM) once-weekly (N = 435) for up to 12 months. Median time on study drug was 365 days on fingolimod 0.5 mg, 354 days on 1.25 mg, and 361 days on interferon beta-1a IM.

The annualized relapse rate was significantly lower in patients treated with fingolimod 0.5 mg than in patients who received interferon beta-1a IM. The key secondary endpoints were number of new and newly enlarging T2 lesions and time to onset of 3-month confirmed disability progression as measured by at least a 1-point increase from baseline in EDSS (0.5-point increase for those with baseline EDSS of 5.5) sustained for 3 months. The number of new and newly enlarging T2 lesions was significantly lower in patients treated with fingolimod than in patients who received interferon beta-1a IM. There was no significant difference in the time to 3-month confirmed disability progression between fingolimod and interferon beta-1a-treated patients at 1 year. The 1.25 mg dose resulted in no additional benefit over the fingolimod 0.5 mg dose. The results for this study are shown in Table 3.

Table 3: Clinical and MRI Results of Study 2
 | Fingolimod Capsules | Interferon beta-1a | p-value
 | 0.5 mg | IM 30 mcg
 | N = 429 | N = 431
Clinical Endpoints
Annualized relapse rate (primary endpoint) | 0.16 | 0.33 | < 0.001
Percentage of patients without relapse | 83% | 70% | < 0.001
Hazard ratio§of disability progression (95% CI) | 0.71 (0.42, 1.21) |  | 0.21
MRI Endpoint
Mean (median) number of new or newly enlarging T2 lesions over 12 months | 1.6 (0) | 2.6 (1.0) | 0.002
Mean (median) number of T1 Gd enhancing lesions at Month 12 | 0.2 (0) | 0.5 (0) | < 0.001

Abbreviation: CI, confidence interval.

All analyses of clinical endpoints were intent-to-treat. MRI analysis used evaluable dataset.

§Hazard ratio is an estimate of the relative risk of having the event of disability progression on fingolimod as compared to control.

Pooled results of Study 1 and Study 2 showed a consistent and statistically significant reduction of annualized relapse rate compared to comparator in subgroups defined by gender, age, prior MS therapy, and disease activity.

14.2 Pediatric Patients (10 to less than 18 Years of Age)

Study 4 (NCT01892722) evaluated the efficacy of once-daily oral doses of fingolimod capsules 0.25 mg or fingolimod capsules 0.5 mg in pediatric patients 10 to less than 18 years of age with relapsing-remitting multiple sclerosis. Study 4 was a 215 patient, double-blind, randomized, clinical trial that compared fingolimod to intramuscular interferon beta-1a. Prior therapy with interferon-beta, dimethyl fumarate, or glatiramer acetate up to the time of randomization was permitted. The study included patients who had experienced at least 1 clinical relapse during the year prior or 2 relapses during the 2 years prior to screening, or evidence of 1 or more Gd-enhancing lesions on MRI within 6 months prior to randomization and had an EDSS score from 0 to 5.5. Neurological evaluations were scheduled at screening, every 3 months, and at the time of suspected relapses. MRI evaluations were performed at screening and every 6 months throughout the study. The primary endpoint was the annualized relapse rate.

At baseline, the median age was 16 years, median disease duration since first symptom was 1.5 years, and median EDSS score was 1.5. One patient received no study drug and is excluded from the analysis of efficacy. Median duration of exposure to study drug was 634 days in the fingolimod group (n = 107) and 547 days in the interferon beta-1a group (n = 107). In the fingolimod group, 6.5% of patients did not complete the study, compared to 18.5% in the interferon beta-1a group.

The primary endpoint, the annualized relapse rate (ARR), was significantly lower in patients treated with fingolimod (0.122) than in patients who received interferon beta-1a (0.675). Relative reduction in ARR was 81.9%. The annualized rate of the number of new or newly enlarged T2 lesions up to month 24 (key secondary endpoint) was significantly lower in patients treated with fingolimod, as was the number of Gd-enhancing T1 lesions per scan up to month 24.

Table 4 summarizes the results of Study 4.

Table 4: Clinical and MRI Results of Study 4
 | Fingolimod 0.25 mg or 0.5 mg PO N = 107 | Interferon beta-1a 30 mcg IM N = 107 | p-value | Relative Reduction
Clinical endpoints
Annualized relapse rate (primary endpoint) | 0.122 | 0.675 | < 0.001§ | 81.9%
Percent of patients remaining relapse-free at 24 months | 86.0% | 45.8%
MRI endpoints
Annualized rate of the number of new or newly enlarging T2 lesions | 4.393 | 9.269 | < 0.001§ | 52.6%
Mean number of Gd-enhancing T1 lesions per scan up to Month 24 | 0.436 | 0.436 | < 0.001§ | 66.0%

Abbreviations: IM, intramuscular; MRI, magnetic resonance imaging; PO, by mouth.

All analyses of clinical endpoints were on full analysis set. MRI analyses used the evaluable dataset.

§Indicates statistical significance vs. Interferon beta-1a IM at two-sided 0.05 level.

16 HOW SUPPLIED/STORAGE AND HANDLING

16.1 How Supplied

0.25 mg TASCENSO ODT orally disintegrating tablets are supplied as follows:
White to off-white, round, orally disintegrating tablet debossed with .

Carton of 30 orally disintegrating tablets containing 3 blister cards of 10 orally disintegrating tablets per blister card

NDC 70709-062-30

0.5 mg TASCENSO ODT orally disintegrating tablets are supplied as follows:

White to off-white, round, orally disintegrating tablet debossed with .

Carton of 30 orally disintegrating tablets containing 3 blister cards of 10 orally disintegrating tablets per blister card

NDC 70709-065-30

16.2 Storage and Handling

TASCENSO ODT should be stored at 20°C to 25°C (68°F to 77°F); excursions permitted to 15°C to 30°C (59°F to 86°F). Protect from moisture. Store in sealed blister pack. Do not open blister until ready to administer.

17 PATIENT COUNSELING INFORMATION

Advise the patient to read the FDA-approved patient labeling (Medication Guide).

Administration

Tell patients not to discontinue TASCENSO ODT without first discussing this with the prescribing healthcare provider. Advise patients to contact their healthcare provider if they accidently take more TASCENSO ODT than prescribed. Advise patients to use dry hands when opening the blister pack. Instruct patients to not push the ODT through the lidding foil, but to peel back the lidding foil and then push the underside [see Dosage and Administration (2.2)].

Cardiac Effects

Advise patients that initiation of TASCENSO ODT treatment results in a transient decrease in heart rate. Inform patients that they will need to be observed in the healthcare professional's office or other facility for at least 6 hours after the first dose, after reinitiation if treatment is interrupted or discontinued for certain periods, and after the dosage is increased [see Dosage and Administration (2.4), Warnings and Precautions (5.1)].

Risk of Infections

Inform patients that they may have an increased risk of infections, some of which could be life-threatening, when taking TASCENSO ODT, and that they should contact their healthcare provider if they develop symptoms of infection. Advise patients that the use of some vaccines should be avoided during treatment with TASCENSO ODT and for 2 months after discontinuation. Recommend to patients that they delay treatment with TASCENSO ODT until after VZV vaccination if they have not had chickenpox or a previous VZV vaccination. Inform patients that prior or concomitant use of drugs that suppress the immune system may increase the risk of infection [see Warnings and Precautions (5.2)].

Progressive Multifocal Leukoencephalopathy

Inform patients that cases of progressive multifocal leukoencephalopathy (PML) have occurred in patients who received fingolimod, the active moiety in TASCENSO ODT. Inform the patient that PML is characterized by a progression of deficits and usually leads to death or severe disability over weeks or months. Instruct the patient of the importance of contacting their healthcare provider if they develop any symptoms suggestive of PML. Inform the patient that typical symptoms associated with PML are diverse, progress over days to weeks, and include progressive weakness on one side of the body or clumsiness of limbs, disturbance of vision, and changes in thinking, memory, and orientation leading to confusion and personality changes [see Warnings and Precautions (5.3)].

Macular Edema

Advise patients that TASCENSO ODT may cause macular edema, and that they should obtain an eye exam near the start of treatment with TASCENSO ODT, have their eyes monitored periodically by an eye care professional while receiving therapy, and contact their healthcare provider if they experience any changes in their vision while taking TASCENSO ODT. Inform patients with diabetes mellitus or a history of uveitis that their risk of macular edema is increased [see Warnings and Precautions (5.4)].

Hepatic Effects

Inform patients that TASCENSO ODT may cause liver injury. Advise patients that they should contact their healthcare provider if they have any unexplained nausea, vomiting, abdominal pain, fatigue, anorexia, or jaundice and/or dark urine [see Warnings and Precautions (5.5)].

Posterior Reversible Encephalopathy Syndrome

Advise patients to immediately report to their healthcare provider any symptoms involving sudden onset of severe headache, altered mental status, visual disturbances, or seizure. Inform patients that delayed treatment could lead to permanent neurological sequelae [see Warnings and Precautions (5.6)].

Respiratory Effects

Advise patients that they should contact their healthcare provider if they experience new onset or worsening of dyspnea [see Warnings and Precautions (5.7)].

Fetal Risk

- Advise pregnant women and females of reproductive potential of the potential risk to a fetus. Advise females to inform their healthcare provider of a known or suspected pregnancy [see Warnings and Precautions (5.8) and Use in Specific Populations (8.1, 8.3)].
- Advise female patients of reproductive potential to use effective contraception during treatment with TASCENSO ODT and for two months after the final dose [see Use in Specific Populations (8.3)].

Severe Increase in Disability After Stopping TASCENSO ODT

Inform patients that severe increase in disability has been reported after discontinuation of fingolimod. Advise patients to contact their healthcare provider if they develop worsening symptoms of MS following discontinuation of TASCENSO ODT [see Warnings and Precautions (5.9)].

Malignancies

Advise patients that the risk of basal cell carcinoma and melanoma is increased with use of fingolimod, the active moiety in TASCENSO ODT, and that cases of squamous cell carcinoma, Merkel cell carcinoma, and Kaposi’s sarcoma have been reported. Advise patients that any suspicious skin lesions should be promptly evaluated. Advise patients to limit exposure to sunlight and ultraviolet light by wearing protective clothing and using a sunscreen with a high protection factor. Inform patients that lymphoma has also occurred in patients receiving fingolimod [see Warnings and Precautions (5.12)].

Persistence of TASCENSO ODT Effects After Drug Discontinuation

Advise patients that TASCENSO ODT remains in the blood and continues to have effects, including decreased blood lymphocyte counts, for up to 2 months following the last dose [see Warnings and Precautions (5.13)].

Hypersensitivity Reactions

Advise patients that TASCENSO ODT may cause hypersensitivity reactions including rash, urticaria, and angioedema. Advise patients to contact their healthcare provider if they have any symptoms associated with hypersensitivity [see Warnings and Precautions (5.14)].

Pregnancy

Instruct patients that if they are pregnant or plan to become pregnant while taking TASCENSO ODT they should inform their physician [see Use in Specific Populations (8.1)].

For full prescribing information, please visit www.tascenso.com.

Manufactured by:
Catalent Pharma Solutions,
Frankland Road, Balgrove,
Swindon, SN5 8RU, United Kingdom

Marketed by:
Cycle Pharmaceuticals Ltd
The Broers Building
21 JJ Thomson Ave
Cambridge, CB3 0FA, United Kingdom

TASCENSO ODT is a trademark of Handa Neuroscience, LLC.

Patented: see www.cyclepharma.com/product-patent-information

MEDICATION GUIDE
TASCENSO ODT® (tuh-SEN-soh ODT)
(fingolimod)
orally disintegrating tablets

Read this Medication Guide before you start taking TASCENSO ODT and each time you get a refill. There may be new information. If you are the parent of a child who is being treated with TASCENSO ODT, the following information applies to your child. This information does not take the place of talking to your healthcare provider about your medical condition or your treatment.

What is the most important information I should know about TASCENSO ODT?
TASCENSO ODT may cause serious side effects, including:
1. Slow heart rate (bradycardia or bradyarrhythmia) when you start taking TASCENSO ODT. TASCENSO ODT can cause your heart rate to slow down, especially after you take your first dose. You will have a test, called an electrocardiogram (ECG), to check the electrical activity of your heart before you take your first dose of TASCENSO ODT.

All adults and children will be observed by a healthcare professional for at least 6 hours after taking their first dose of TASCENSO ODT. Children should also be observed by a healthcare professional for at least 6 hours after taking their first dose of 0.5 mg of TASCENSO ODT when switching from the 0.25 mg dose.

After you take your first dose of TASCENSO ODT, and after a child takes their first dose of 0.5 mg of TASCENSO ODT when switching from the 0.25 mg dose:

- Your pulse and blood pressure should be checked every hour.
- You should be observed by a healthcare professional to see if you have any serious side effects. If your heart rate slows down too much, you may have symptoms, such as:
  - dizziness
  - tiredness
  - feeling like your heart is beating slowly or skipping beats
  - chest pain
- If you have any symptoms of slow heart rate, they will usually happen during the first 6 hours after your first dose of TASCENSO ODT. Symptoms can happen up to 24 hours after you take your first dose of TASCENSO ODT.
- 6 hours after you take your first dose of TASCENSO ODT you will have another ECG. If your ECG shows any heart problems or if your heart rate is still too low or continues to decrease, you will continue to be observed.
- If you have any serious side effects after your first dose of TASCENSO ODT, especially those that require treatment with other medicines, you will stay in the medical facility to be observed overnight. You will also be observed for any serious side effects for at least 6 hours after you take your second dose of TASCENSO ODT the next day.
- If you have certain types of heart problems, or if you are taking certain types of medicines that can affect your heart, you will be observed overnight after you take your first dose of TASCENSO ODT.

Your slow heart rate will usually return to normal within 1 month after you start taking TASCENSO ODT. Call your healthcare provider or go to the nearest hospital emergency room right away if you have any symptoms of a slow heart rate.

If you miss 1 or more doses of TASCENSO ODT, you may need to be observed by a healthcare professional when you take your next dose. Call your healthcare provider if you miss a dose of TASCENSO ODT. See "How should I take TASCENSO ODT?"

2. Pregnancy. Please consult your healthcare provider before getting pregnant. You should avoid becoming pregnant while taking TASCENSO ODT or in the two months after you stop taking it because of the risk of harm to the baby.

3. Infections. TASCENSO ODT can increase your risk of serious infections that can be life-threatening and cause death. You should not receive live vaccines during treatment with TASCENSO ODT and for 2 months after you stop taking TASCENSO ODT. Talk to your healthcare provider before you receive a vaccine during treatment and for 2 months after treatment with TASCENSO ODT. If you receive a live vaccine, you may get the infection the vaccine was meant to prevent. Vaccines may not work as well when given during treatment with TASCENSO ODT.

Human Papilloma Virus (HPV). Due to risk of HPV infection please consult your healthcare provider for routine pap smear.

TASCENSO ODT lowers the number of white blood cells (lymphocytes) in your blood. This will usually go back to normal within 2 months of stopping treatment. Your healthcare provider may do a blood test to check your white blood cells before you start taking TASCENSO ODT. Call your healthcare provider right away if you have any of these symptoms of an infection during treatment with TASCENSO ODT, and for 2 months after your last dose of TASCENSO ODT:

- fever
- tiredness
- body aches
- chills
- nausea
- vomiting
- headache with fever, neck stiffness, sensitivity to light, nausea, or confusion (these may be symptoms of meningitis, an infection of the lining around your brain and spine)

4. Progressive multifocal leukoencephalopathy (PML). PML is a rare brain infection that usually leads to death or severe disability. If PML happens, it usually happens in people with weakened immune systems but has happened in people who do not have weakened immune systems. Symptoms of PML get worse over days to weeks.

Call your healthcare provider right away if you have any new or worsening symptoms of PML, that have lasted several days, including:

- weakness on 1 side of your body
- loss of coordination in your arms and legs
- decreased strength
- problems with balance
- changes in your vision
- changes in your thinking or memory
- confusion
- changes in your personality

5. A problem with your vision called macular edema. Macular edema can cause some of the same vision symptoms as a multiple sclerosis (MS) attack (optic neuritis). You may not notice any symptoms with macular edema. If macular edema happens, it usually starts in the first 3 to 4 months after you start taking fingolimod, the active ingredient in TASCENSO ODT, but can happen at any time. Your healthcare provider should test your vision around the time you start taking TASCENSO ODT, 3 to 4 months after you start taking TASCENSO ODT, periodically while you continue taking TASCENSO ODT, and any time you notice vision changes during treatment with TASCENSO ODT. Your risk of macular edema is higher if you have diabetes or have had an inflammation of your eye called uveitis.

Call your healthcare provider right away if you have any of the following symptoms:

- blurriness or shadows in the center of your vision
- a blind spot in the center of your vision
- sensitivity to light
- unusually colored (tinted) vision

What is TASCENSO ODT?
TASCENSO ODT is a prescription medicine used to treat relapsing forms of multiple sclerosis (MS), to include clinically isolated syndrome, relapsing-remitting disease, and active secondary progressive disease, in adults and children 10 years of age and older.

It is not known if TASCENSO ODT is safe and effective in children under 10 years of age.

Who should not take TASCENSO ODT?
Do not take TASCENSO ODT if you:

- have had a heart attack, unstable angina, stroke or mini-stroke (transient ischemic attack or TIA) or certain types of heart failure in the last 6 months.
- have certain types of irregular or abnormal heartbeat (arrhythmia), including patients in whom a heart finding called prolonged QT is seen on ECG before starting TASCENSO ODT.
- have a heart rhythm problem that needs treatment with certain medicines.
- are allergic to fingolimod or any of the ingredients in TASCENSO ODT. See the end of this leaflet for a complete list of ingredients in TASCENSO ODT. Symptoms of an allergic reaction may include rash, itchy hives, or swelling of the lips, tongue or face.
- taking other products containing fingolimod, the active ingredient in TASCENSO ODT.

Talk to your healthcare provider before taking TASCENSO ODT if you have any of these conditions, or do not know if you have any of these conditions.

What should I tell my healthcare provider before taking TASCENSO ODT?
Before you take TASCENSO ODT, tell your healthcare provider about all your medical conditions, including if you had or now have:

- an irregular or abnormal heartbeat (arrhythmia).
- a history of stroke or mini-stroke.
- heart problems, including heart attack or angina.
- a history of repeated fainting (syncope).
- a fever or infection, or you are unable to fight infections due to a disease or take or have taken medicines that lower your immune system.
- recently received a vaccine or are scheduled to receive a vaccine.
- chickenpox or have received the vaccine for chickenpox. Your healthcare provider may do a blood test for chickenpox virus. You may need to get the full course of the vaccine for chickenpox and then wait 1 month before you start taking TASCENSO ODT.
- your child has completed their vaccination schedule. Your child needs to have completed their vaccination schedule before starting treatment with TASCENSO ODT.
- eye problems, especially an inflammation of the eye called uveitis.
- diabetes.
- breathing problems, including during your sleep.
- liver problems.
- high blood pressure.
- any type of skin cancer, including basal cell carcinoma (BCC), melanoma or squamous cell carcinoma (SCC).
- are pregnant or plan to become pregnant. TASCENSO ODT may harm your unborn baby. Talk to your healthcare provider if you are pregnant or are planning to become pregnant. Tell your healthcare provider right away if you become pregnant while taking TASCENSO ODT or if you become pregnant within 2 months after you stop taking TASCENSO ODT.
  - You should stop taking TASCENSO ODT 2 months before trying to become pregnant.
  - If you are a female who can become pregnant, you should use effective birth control during your treatment with TASCENSO ODT and for at least 2 months after you stop taking TASCENSO ODT.
- are breastfeeding or plan to breastfeed. It is not known if TASCENSO ODT passes into your breast milk. Talk to your healthcare provider about the best way to feed your baby if you take TASCENSO ODT.

Tell your healthcare provider about all the medicines you take or have recently taken, including prescription and over-the-counter medicines, vitamins, and herbal supplements.

Especially tell your healthcare provider if you take medicines that affect your immune system, including corticosteroids, or have taken them in the past.

Know the medicines you take. Keep a list of your medicines with you to show your healthcare provider and pharmacist when you get a new medicine.

Using TASCENSO ODT and other medicines together may affect each other causing serious side effects.

Do not take TASCENSO ODT with Gilenya or other medicines containing fingolimod.

How should I take TASCENSO ODT?

- Adults and children will be observed by a healthcare professional for at least 6 hours after taking their first dose of fingolimod. Children should also be observed by a healthcare professional for at least 6 hours after taking their first dose of 0.5 mg of TASCENSO ODT when switching from the 0.25 mg dose. See "What is the most important information I should know about TASCENSO ODT?"
- Take TASCENSO ODT exactly as your healthcare provider tells you to take it.
- Take TASCENSO ODT 1 time each day.
- TASCENSO ODT may be taken with or without water.
- TASCENSO ODT may be taken with or without food.
- Store the TASCENSO ODT in the sealed blister pack until ready to take.
- Do not push the TASCENSO ODT through the foil.
- Use dry hands when opening the blister pack.
- Peel back the foil from 1 blister pack, then push the bottom of the blister pack to release the TASCENSO ODT and gently remove it.
- Take the orally disintegrating tablet (ODT) immediately after opening the blister pack.
- Place the ODT on the tongue and allow it to dissolve before swallowing.
- If you take too much TASCENSO ODT, call your healthcare provider or go to the nearest hospital emergency room right away.
- Do not stop taking TASCENSO ODT without talking with your healthcare provider first.
- Call your healthcare provider right away if you miss a dose of TASCENSO ODT. You may need to be observed by a healthcare professional for at least 6 hours when you take your next dose. If you need to be observed by a healthcare professional when you take your next dose of TASCENSO ODT you will have:
  - an ECG before you take your dose
  - hourly pulse and blood pressure measurements after you take the dose
  - an ECG 6 hours after your dose

See "What is the most important information I should know about TASCENSO ODT?"

What are possible side effects of TASCENSO ODT?
TASCENSO ODT may cause serious side effects, including:

- See "What is the most important information I should know about TASCENSO ODT?"
- swelling and narrowing of the blood vessels in your brain. A condition called PRES (Posterior Reversible Encephalopathy Syndrome) has happened rarely in adults taking fingolimod, the active ingredient in TASCENSO ODT. Symptoms of PRES usually get better when you stop taking TASCENSO ODT.
  However, if left untreated, it may lead to a stroke. Call your healthcare provider right away if you have any of the following symptoms:
  - sudden severe headache
  - sudden confusion
  - sudden loss of vision or other changes in your vision
  - seizure
- liver damage. TASCENSO ODT may cause liver damage. Your healthcare provider should do blood tests to check your liver before you start taking TASCENSO ODT and periodically during treatment. Call your healthcare provider right away if you have any of the following symptoms of liver damage:
  - nausea
  - vomiting
  - stomach pain
  - tiredness
  - loss of appetite
  - your skin or the whites of your eyes turn yellow
  - dark urine
- breathing problems. Some people who take TASCENSO ODT have shortness of breath. Call your healthcare provider right away if you have new or worsening breathing problems.
- severe worsening of multiple sclerosis after stopping TASCENSO ODT. When TASCENSO ODT is stopped, symptoms of MS can return and become worse compared to before or during treatment. Many people who have worsening of MS symptoms after stopping TASCENSO ODT do not return to the level of function that they had before stopping TASCENSO ODT. This worsening happens most often within 12 weeks after stopping TASCENSO ODT but can happen later. Always talk to your healthcare provider before you stop taking TASCENSO ODT for any reason. Tell your healthcare provider if you have worsening symptoms of MS after stopping TASCENSO ODT.
- increased blood pressure. Your healthcare provider should check your blood pressure during treatment with TASCENSO ODT.
- types of skin cancer, including basal cell carcinoma, melanoma, and squamous cell carcinoma. Tell your healthcare provider if you have any changes in the appearance of your skin, including changes in a mole, a new darkened area on your skin, a sore that does not heal, or growths on your skin, such as a bump that may be shiny, pearly white, skin-colored, or pink. Your healthcare provider should check your skin for any changes at the start of and during treatment with TASCENSO ODT. Limit the amount of time you spend in sunlight and ultraviolet (UV) light. Wear protective clothing and use a sunscreen with a high sun protection factor.
- allergic reactions. Call your healthcare provider if you have symptoms of an allergic reaction, including a rash, itchy hives, or swelling of the lips, tongue or face.

The most common side effects of TASCENSO ODT include:

- headache
- abnormal liver tests
- diarrhea
- cough
- flu
- inflammation of the sinuses (sinusitis)
- back pain
- stomach-area (abdominal) pain
- pain in arms or legs

Tell your healthcare provider if you have any side effect that bothers you or that does not go away.
These are not all of the possible side effects of TASCENSO ODT. For more information, ask your healthcare provider or pharmacist. Call your doctor for medical advice about side effects. You may report side effects to FDA at 1-800-FDA-1088.

How should I store TASCENSO ODT?

- Store TASCENSO ODT in the blister pack in a dry place.
- Store TASCENSO ODT at room temperature between 68°F to 77°F (20°C to 25°C).
- Do not open the blister pack until ready to take TASCENSO ODT.
- Keep TASCENSO ODT and all medicines out of the reach of children.

General information about the safe and effective use of TASCENSO ODT.
Medicines are sometimes prescribed for purposes other than those listed in a Medication Guide. Do not use TASCENSO ODT for a condition for which it was not prescribed. Do not give TASCENSO ODT to other people, even if they have the same symptoms that you have. It may harm them. This Medication Guide summarizes the most important information about TASCENSO ODT. If you would like more information, talk with your healthcare provider. You can ask your healthcare provider or pharmacist for information about TASCENSO ODT that is written for health professionals.

What are the ingredients in TASCENSO ODT?
0.25 mg orally disintegrating tablets
Active ingredient: fingolimod lauryl sulfate.
Inactive ingredients: gelatin, mannitol, medium-chain triglycerides, sodium chloride, and sodium lauryl sulfate.

0.5 mg orally disintegrating tablets

Active ingredient: fingolimod lauryl sulfate.

Inactive ingredients: gelatin, mannitol, medium-chain triglycerides, sodium chloride, and sodium lauryl sulfate.
TASCENSO ODT is a trademark of Handa Neuroscience, LLC.
Manufactured by: Catalent Pharma Solutions, Swindon, United Kingdom
Marketed by: Cycle Pharmaceuticals Ltd, Cambridge, CB3 0FA, United Kingdom
For more information, go to www.tascenso.com or call +1 (888) 533-1625

This Medication Guide has been approved by the U.S. Food and Drug Administration

Revised: 1/2025

PRINCIPAL DISPLAY PANEL - 0.25 mg Tablet Carton containing Blisters

Rx Only

FOR ORAL USE ONLY

NDC 70709-062-30

CYCLE PHARMA

TASCENSO ODT® (fingolimod)

orally disintegrating tablets 0.25 mg

Contains 30 tablets
(3 blister cards of 10 tablets)

PHARMACIST: Provide the accompanying

Medication Guide to each patient.

PRINCIPAL DISPLAY PANEL - 0.5 mg Tablet Carton containing Blisters

Rx Only

FOR ORAL USE ONLY

NDC 70709-065-30

CYCLE PHARMA

TASCENSO ODT® (fingolimod)

orally disintegrating tablets 0.5 mg

Contains 30 tablets
(3 blister cards of 10 tablets)

PHARMACIST: Provide the accompanying

Medication Guide to each patient.